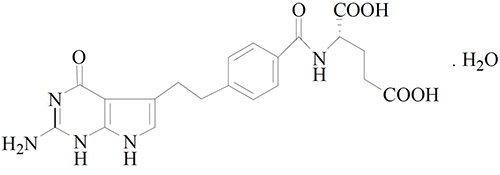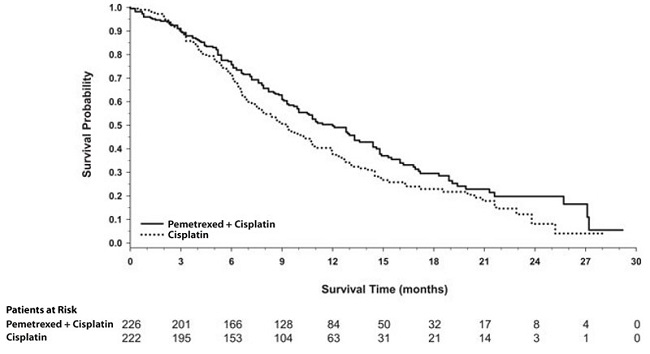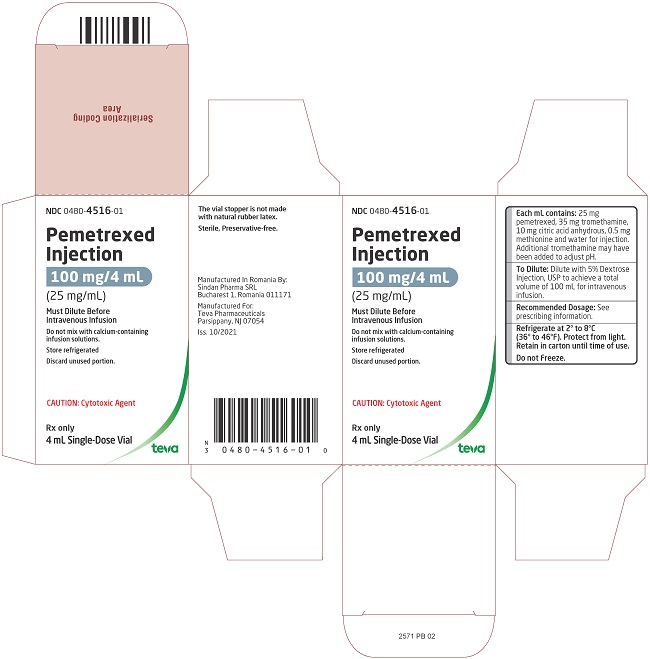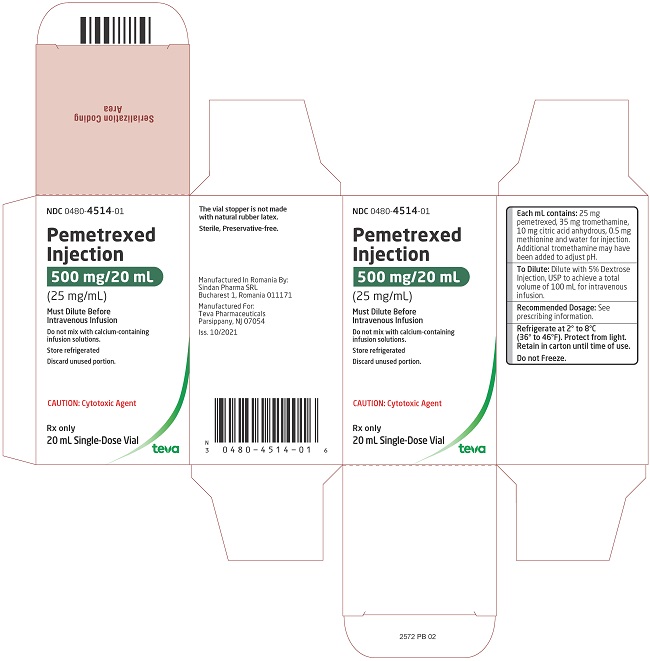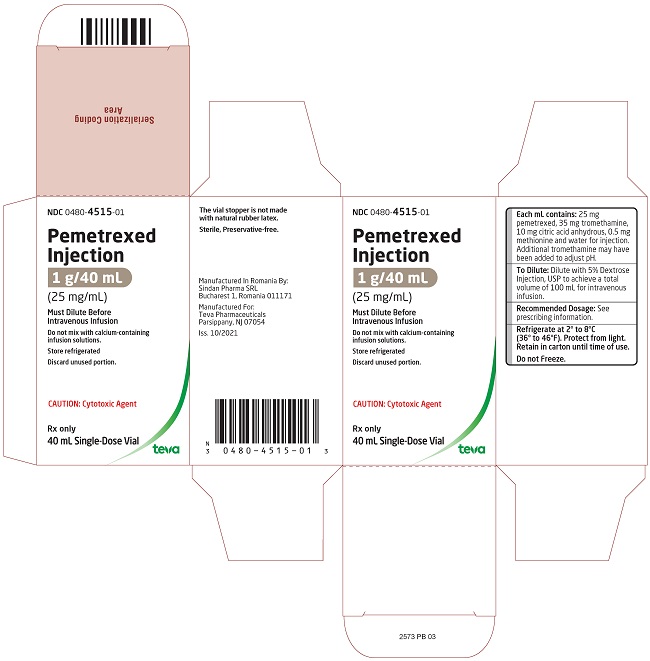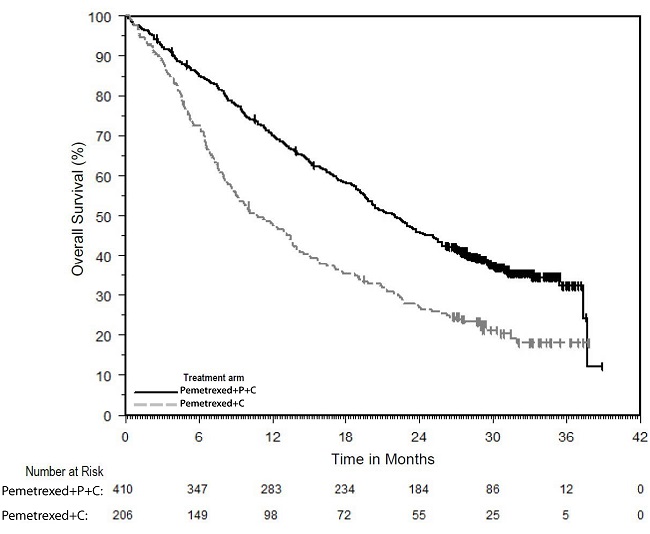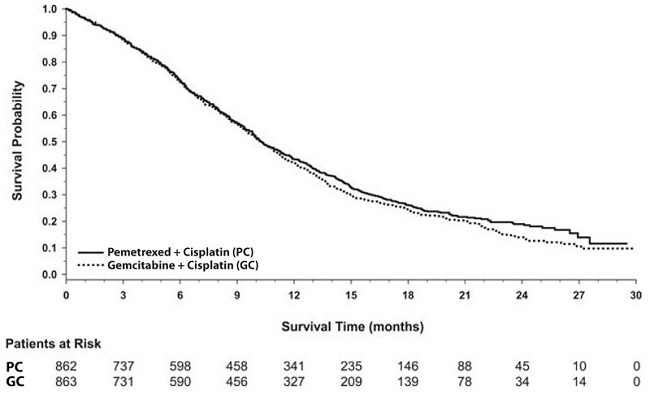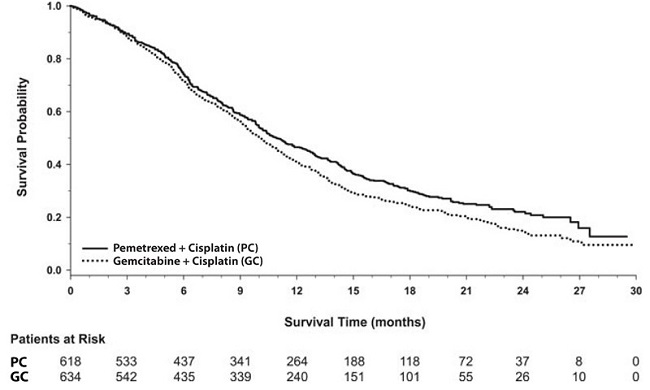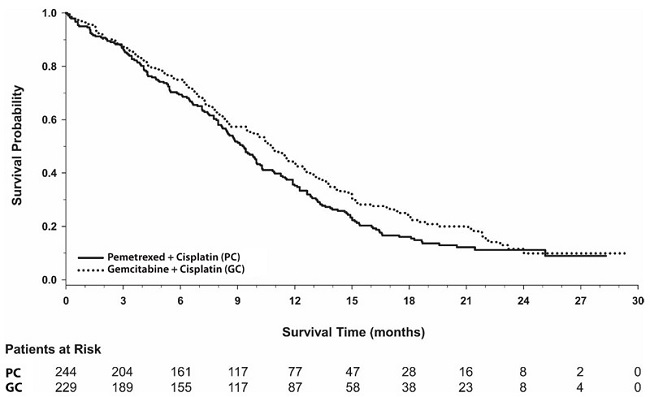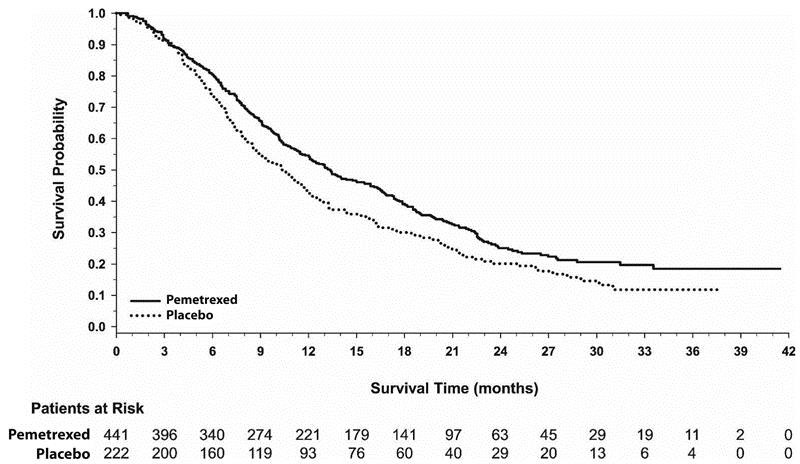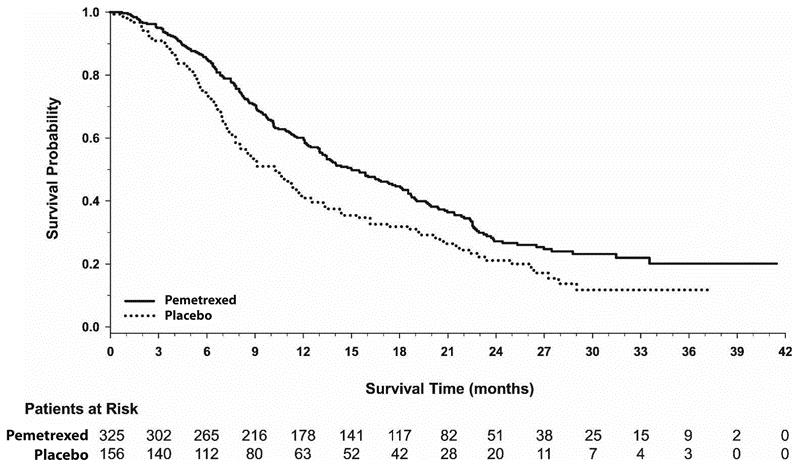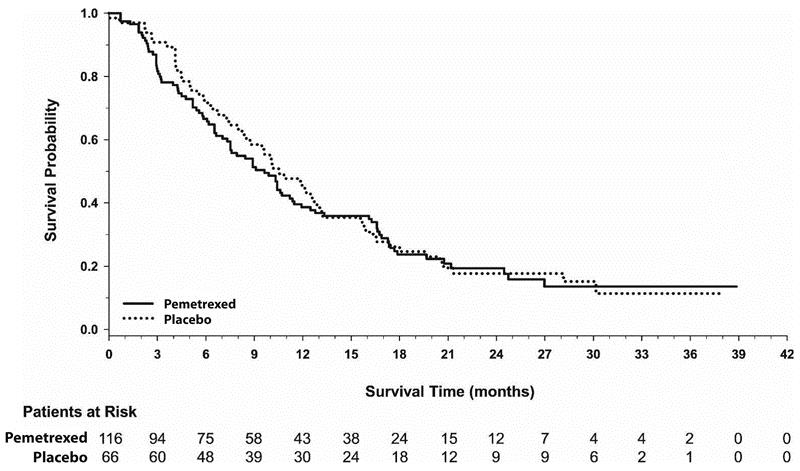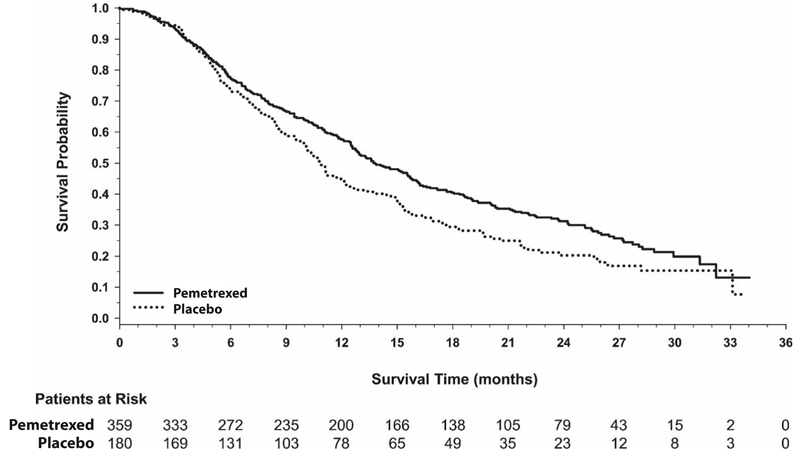 DRUG LABEL: Pemetrexed
NDC: 0480-4516 | Form: SOLUTION, CONCENTRATE
Manufacturer: Teva Pharmaceuticals, Inc.
Category: prescription | Type: HUMAN PRESCRIPTION DRUG LABEL
Date: 20221201

ACTIVE INGREDIENTS: PEMETREXED MONOHYDRATE 25 mg/1 mL
INACTIVE INGREDIENTS: TROMETHAMINE; ANHYDROUS CITRIC ACID; METHIONINE; WATER

HIGHLIGHTS OF PRESCRIBING INFORMATION

These highlights do not include all the information needed to use PEMETREXED INJECTION safely and effectively. See full prescribing information for PEMETREXED INJECTION.
PEMETREXED injection, for intravenous use
Initial U.S. Approval: 2004

RECENT MAJOR CHANGES

Indications and Usage (1.1) | 11/2022
Indications and Usage (1.2) | 11/2022
Dosage and Administration (2.1, 2.2, 2.6) | 11/2022
Warnings and precautions (5.1, 5.2) | 11/2022

1 INDICATIONS AND USAGE

Pemetrexed Injection is a folate analog metabolic inhibitor indicated:

- in combination with pembrolizumab and platinum chemotherapy, for the initial treatment of patients with metastatic non-squamous non-small cell lung cancer (NSCLC), with no epidermal growth factor receptor (EGFR) or anaplastic lymphoma kinase (ALK) genomic tumor aberrations. (1.1)
- in combination with cisplatin for the initial treatment of patients with locally advanced or metastatic, non-squamous NSCLC. (1.1)
- as a single agent for the maintenance treatment of patients with locally advanced or metastatic, non-squamous NSCLC whose disease has not progressed after four cycles of platinum-based first-line chemotherapy. (1.1)
- as a single agent for the treatment of patients with recurrent, metastatic non-squamous, NSCLC after prior chemotherapy. (1.1)

Limitations of Use:

Pemetrexed Injection is not indicated for the treatment of patients with squamous cell, non-small cell lung cancer. (1.1)

- initial treatment, in combination with cisplatin, of patients with malignant pleural mesothelioma whose disease is unresectable or who are otherwise not candidates for curative surgery. (1.2)

2 DOSAGE AND ADMINISTRATION

- The recommended dose of Pemetrexed Injection administered with pembrolizumab and platinum chemotherapy in patients with a creatinine clearance (calculated by Cockcroft-Gault equation) of 45 mL/min or greater is 500 mg/m^2 as an intravenous infusion over 10 minutes, administered after pembrolizumab and prior to platinum chemotherapy, on Day 1 of each 21-day cycle. (2.1)
- The recommended dose of Pemetrexed Injection, administered as a single agent or with cisplatin, in patients with creatinine clearance of 45 mL/minute or greater is 500 mg/m^2 as an intravenous infusion over 10 minutes on Day 1 of each 21-day cycle. (2.1, 2.2)
- Initiate folic acid 400 mcg to 1000 mcg orally, once daily, beginning 7 days prior to the first dose of Pemetrexed Injection and continue until 21 days after the last dose of Pemetrexed Injection. (2.4)
- Administer vitamin B12, 1 mg intramuscularly, 1 week prior to the first dose of Pemetrexed Injection and every 3 cycles. (2.4)
- Administer dexamethasone 4 mg orally, twice daily the day before, the day of, and the day after Pemetrexed Injection administration. (2.4)

3 DOSAGE FORMS AND STRENGTHS

Injection: 100 mg/4 mL, 500 mg/20 mL or 1 g/40 mL solution in single-dose vials (3)

4 CONTRAINDICATIONS

History of severe hypersensitivity reaction to pemetrexed. (4)

5 WARNINGS AND PRECAUTIONS

- Myelosuppression: Can cause severe bone marrow suppression resulting in cytopenia and an increased risk of infection. Do not administer pemetrexed when the absolute neutrophil count is less than 1500 cells/mm^3 and platelets are less than 100,000 cells/mm^3. Initiate supplementation with oral folic acid and intramuscular vitamin B12 to reduce the severity of hematologic and gastrointestinal toxicity of pemetrexed. (2.4, 5.1)
- Renal Failure: Can cause severe, and sometimes fatal, renal failure. Do not administer when creatinine clearance is less than 45 mL/min. (2.3, 5.2)
- Bullous and Exfoliative Skin Toxicity: Permanently discontinue for severe and life-threatening bullous, blistering or exfoliating skin toxicity. (5.3)
- Interstitial Pneumonitis: Withhold for acute onset of new or progressive unexplained pulmonary symptoms. Permanently discontinue if pneumonitis is confirmed. (5.4)
- Radiation Recall: Can occur in patients who received radiation weeks to years previously; permanently discontinue for signs of radiation recall. (5.5)
- Embryo-Fetal Toxicity: Can cause fetal harm. Advise patients of the potential risk to a fetus and to use effective contraception. (5.7, 8.1, 8.3)

6 ADVERSE REACTIONS

- The most common adverse reactions (incidence ≥20%) of pemetrexed, when administered as a single agent are fatigue, nausea, and anorexia. (6.1)
- The most common adverse reactions (incidence ≥20%) of pemetrexed when administered with cisplatin are vomiting, neutropenia, anemia, stomatitis/pharyngitis, thrombocytopenia, and constipation. (6.1)
- The most common adverse reactions (incidence ≥20%) of pemetrexed when administered in combination with pembrolizumab and platinum chemotherapy are fatigue/asthenia, nausea, constipation, diarrhea, decreased appetite, rash, vomiting, cough, dyspnea, and pyrexia. (6.1)

To report SUSPECTED ADVERSE REACTIONS, contact Teva at 1-888-838-2872 or FDA at 1-800-FDA-1088 or www.fda.gov/medwatch.

7 DRUG INTERACTIONS

Ibuprofen increased risk of pemetrexed toxicity in patients with mild to moderate renal impairment. Modify the ibuprofen dosage as recommended for patients with a creatinine clearance between 45 mL/min and 79 mL/min. (2.5, 5.6, 7)

8 USE IN SPECIFIC POPULATIONS

Lactation: Advise not to breastfeed. (8.2)

FULL PRESCRIBING INFORMATION

RECENT MAJOR CHANGES

Indications and Usage (1.1) | 11/2022
Indications and Usage (1.2) | 11/2022
Dosage and Administration (2.1, 2.2, 2.6) | 11/2022
Warnings and precautions (5.1, 5.2) | 11/2022

1 INDICATIONS AND USAGE

1.1 Non-Squamous Non-Small Cell Lung Cancer (NSCLC)

Pemetrexed Injection is indicated:

- in combination with pembrolizumab and platinum chemotherapy, for the initial treatment of patients with metastatic non-squamous non-small cell lung cancer (NSCLC), with no epidermal growth factor receptor (EGFR) or anaplastic lymphoma kinase (ALK) genomic tumor aberrations.
- in combination with cisplatin for the initial treatment of patients with locally advanced or metastatic, non- squamous NSCLC.
- as a single agent for the maintenance treatment of patients with locally advanced or metastatic, non-squamous NSCLC whose disease has not progressed after four cycles of platinum-based first-line chemotherapy.
- as a single agent for the treatment of patients with recurrent, metastatic non-squamous, NSCLC after prior chemotherapy.

Limitations of Use: Pemetrexed Injection is not indicated for the treatment of patients with squamous cell, non-small cell lung cancer [see Clinical Studies (14.1)].

1.2 Mesothelioma

Pemetrexed Injection is indicated, in combination with cisplatin, for the initial treatment of patients with malignant pleural mesothelioma whose disease is unresectable or who are otherwise not candidates for curative surgery.

2 DOSAGE AND ADMINISTRATION

2.1 Recommended Dosage for Non-Squamous NSCLC

- The recommended dose of Pemetrexed Injection when administered with pembrolizumab and platinum chemotherapy for the initial treatment of metastatic non-squamous NSCLC in patients with a creatinine clearance (calculated by Cockcroft-Gault equation) of 45 mL/min or greater is 500 mg/m^2 as an intravenous infusion over 10 minutes administered after pembrolizumab and prior to carboplatin or cisplatin on Day 1 of each 21-day cycle for 4 cycles. Following completion of platinum-based therapy, treatment with Pemetrexed Injection with or without pembrolizumab is administered until disease progression or unacceptable toxicity. Please refer to the full prescribing information for pembrolizumab and for carboplatin or cisplatin.
- The recommended dose of Pemetrexed Injection when administered with cisplatin for initial treatment of locally advanced or metastatic non-squamous NSCLC in patients with a creatinine clearance (calculated by Cockcroft-Gault equation) of 45 mL/min or greater is 500 mg/m^2 as an intravenous infusion over 10 minutes administered prior to cisplatin on Day 1 of each 21-day cycle for up to six cycles in the absence of disease progression or unacceptable toxicity.
- The recommended dose of Pemetrexed Injection for maintenance treatment of non-squamous NSCLC in patients with a creatinine clearance (calculated by Cockcroft-Gault equation) of 45 mL/min or greater is 500 mg/m^2 as an intravenous infusion over 10 minutes on Day 1 of each 21-day cycle until disease progression or unacceptable toxicity after four cycles of platinum-based first-line chemotherapy.
- The recommended dose of Pemetrexed Injection for treatment of recurrent non-squamous NSCLC in patients with a creatinine clearance (calculated by Cockcroft-Gault equation) of 45 mL/min or greater is 500 mg/m^2 as an intravenous infusion over 10 minutes on Day 1 of each 21-day cycle until disease progression or unacceptable toxicity.

2.2 Recommended Dosage for Mesothelioma

- The recommended dose of Pemetrexed Injection when administered with cisplatin in patients with a creatinine clearance (calculated by Cockcroft-Gault equation) of 45 mL/min or greater is 500 mg/m^2 as an intravenous infusion over 10 minutes on Day 1 of each 21-day cycle until disease progression or unacceptable toxicity.

2.3 Renal Impairment

- Pemetrexed Injection dosing recommendations are provided for patients with a creatinine clearance (calculated by Cockcroft-Gault equation) of 45 mL/min or greater [see Dosage and Administration (2.1, 2.2)]. There is no recommended dose for patients whose creatinine clearance is less than 45 mL/min [see Use in Specific Populations (8.6)].

2.4 Premedication and Concomitant Medications to Mitigate Toxicity

Vitamin Supplementation

- Initiate folic acid 400 mcg to 1000 mcg orally once daily, beginning 7 days before the first dose of Pemetrexed Injection and continuing until 21 days after the last dose of Pemetrexed Injection [see Warnings and Precautions (5.1)].
- Administer vitamin B12, 1 mg intramuscularly, 1 week prior to the first dose of Pemetrexed Injection and every 3 cycles thereafter. Subsequent vitamin B12 injections may be given the same day as treatment with Pemetrexed Injection [see Warnings and Precautions (5.1)]. Do not substitute oral vitamin B12 for intramuscular vitamin B12.

Corticosteroids

- Administer dexamethasone 4 mg orally twice daily for three consecutive days, beginning the day before each Pemetrexed Injection administration.

2.5 Dosage Modification of Ibuprofen in Patients with Mild to Moderate Renal Impairment Receiving Pemetrexed Injection

In patients with creatinine clearances between 45 mL/min and 79 mL/min, modify administration of ibuprofen as follows [see Warnings and Precautions (5.6), Drug Interactions (7) and Clinical Pharmacology (12.3)]:

- Avoid administration of ibuprofen for 2 days before, the day of, and 2 days following administration of Pemetrexed Injection.
- Monitor patients more frequently for myelosuppression, renal, and gastrointestinal toxicity, if concomitant administration of ibuprofen cannot be avoided.

2.6 Dosage Modifications for Adverse Reactions

Obtain complete blood count on Days 1, 8, and 15 of each cycle. Assess creatinine clearance prior to each cycle. Do not administer Pemetrexed Injection if the creatinine clearance is less than 45 mL/min.

Delay initiation of the next cycle of Pemetrexed Injection until:

- recovery of non-hematologic toxicity to Grade 0-2,
- absolute neutrophil count (ANC) is 1500 cells/mm^3 or higher, and
- platelet count is 100,000 cells/mm^3 or higher.

Upon recovery, modify the dosage of Pemetrexed Injection in the next cycle as specified in Table 1.

For dosing modifications for cisplatin, carboplatin, or pembrolizumab, refer to their prescribing information.

Table 1: Recommended Dosage Modifications for Adverse Reactionsa
Toxicity in Most Recent Treatment Cycle | Pemetrexed Injection Dose Modification for Next Cycle
Myelosuppressive toxicity [see Warnings and Precautions (5.1)]
ANC less than 500/mm^3 and platelets greater than or equal to 50,000/mm^3; OR; Platelet count less than 50,000/mm^3 without bleeding. | 75% of previous dose
Platelet count less than 50,000/mm^3 with bleeding | 50% of previous dose
Recurrent Grade 3 or 4 myelosuppression after 2 dose reductions | Discontinue
Non-hematologic toxicity
Any Grade 3 or 4 toxicities EXCEPT mucositis or neurologic toxicity; OR; Diarrhea requiring hospitalization | 75% of previous dose
Grade 3 or 4 mucositis | 50% of previous dose
Renal toxicity [see Warnings and Precautions (5.2)] | Withhold until creatinine; clearance is 45 mL/min or greater
Grade 3 or 4 neurologic toxicity | Permanently discontinue
Recurrent Grade 3 or 4 non-hematologic toxicity after 2 dose reductions | Permanently discontinue
Severe and life-threatening Skin Toxicity [see Warnings and Precautions (5.3)] | Permanently discontinue
Interstitial Pneumonitis [see Warnings and Precautions (5.4)] | Permanently discontinue
a National Cancer Institute Common Toxicity Criteria for Adverse Events version 2 (NCI CTCAE v2).

2.7 Preparation for Administration

- Pemetrexed Injection is a hazardous drug. Follow applicable special handling and disposal procedures.^1
- Calculate the dose of Pemetrexed Injection and determine the number of vials needed.
- Withdraw the calculated dose of Pemetrexed Injection from the vial(s) and discard vial with any unused portion.
- Dilute Pemetrexed Injection with 5% Dextrose Injection, USP to achieve a total volume of 100 mL for intravenous infusion.
- Administer diluted solution via an 0.2 µm in-line filter.
- Parenteral drug products should be inspected visually for particulate matter and discoloration prior to administration, whenever solution and container permit. If particulate matter is observed, do not administer.

Store diluted solution under refrigerated conditions [2° to 8°C (36° to 46°F)] for no more than 14 days from the time of dilution and at room temperature for not more than 8 hours from the time of dilution.

3 DOSAGE FORMS AND STRENGTHS

Injection: Pemetrexed Injection is a clear, colorless to slightly yellowish or slightly yellow-greenish solution available in sterile single-dose vials containing 100 mg/4 mL, 500 mg/20 mL, and 1 g/40 mL of pemetrexed.

4 CONTRAINDICATIONS

Pemetrexed is contraindicated in patients with a history of severe hypersensitivity reaction to pemetrexed [see Adverse Reactions (6.1)].

5 WARNINGS AND PRECAUTIONS

5.1 Myelosuppression and Increased Risk of Myelosuppression without Vitamin Supplementation

Pemetrexed can cause severe myelosuppression resulting in a requirement for transfusions and which may lead to neutropenic infection. The risk of myelosuppression is increased in patients who do not receive vitamin supplementation. In Study JMCH, incidences of Grade 3-4 neutropenia (38% versus 23%), thrombocytopenia (9% versus 5%), febrile neutropenia (9% versus 0.6%), and neutropenic infection (6% versus 0) were higher in patients who received pemetrexed plus cisplatin without vitamin supplementation as compared to patients who were fully supplemented with folic acid and vitamin B12 prior to and throughout pemetrexed plus cisplatin treatment.

Initiate supplementation with oral folic acid and intramuscular vitamin B12 prior to the first dose of Pemetrexed Injection; continue vitamin supplementation during treatment and for 21 days after the last dose of Pemetrexed Injection to reduce the severity of hematologic and gastrointestinal toxicity of Pemetrexed Injection [see Dosage and Administration (2.4)]. Obtain a complete blood count at the beginning of each cycle. Do not administer Pemetrexed Injection until the ANC is at least 1500 cells/mm^3 and platelet count is at least 100,000 cells/mm^3. Permanently reduce Pemetrexed Injection in patients with an ANC of less than 500 cells/mm^3 or platelet count of less than 50,000 cells/mm^3 in previous cycles [see Dosage and Administration (2.6)].

In Studies JMDB and JMCH, among patients who received vitamin supplementation, incidence of Grade 3-4 neutropenia was 15% and 23%, the incidence of Grade 3-4 anemia was 6% and 4%, and incidence of Grade 3-4 thrombocytopenia was 4% and 5%, respectively. In Study JMCH, 18% of patients in the pemetrexed arm required red blood cell transfusions compared to 7% of patients in the cisplatin arm [see Adverse Reactions (6.1)]. In Studies JMEN, PARAMOUNT, and JMEI, where all patients received vitamin supplementation, incidence of Grade 3-4 neutropenia ranged from 3% to 5%, and incidence of Grade 3-4 anemia ranged from 3% to 5%.

5.2 Renal Failure

Pemetrexed can cause severe, and sometimes fatal, renal toxicity. The incidences of renal failure in clinical studies in which patients received pemetrexed with cisplatin were: 2.1% in Study JMDB and 2.2% in Study JMCH. The incidence of renal failure in clinical studies in which patients received pemetrexed as a single agent ranged from 0.4% to 0.6% (Studies JMEN, PARAMOUNT, and JMEI [see Adverse Reactions (6.1)]. Determine creatinine clearance before each dose and periodically monitor renal function during treatment with pemetrexed. Withhold pemetrexed in patients with a creatinine clearance of less than 45 mL/minute [see Dosage and Administration (2.3)].

5.3 Bullous and Exfoliative Skin Toxicity

Serious and sometimes fatal, bullous, blistering and exfoliative skin toxicity, including cases suggestive of Stevens- Johnson Syndrome/Toxic epidermal necrolysis can occur with pemetrexed. Permanently discontinue pemetrexed for severe and life-threatening bullous, blistering or exfoliating skin toxicity.

5.4 Interstitial Pneumonitis

Serious interstitial pneumonitis, including fatal cases, can occur with Pemetrexed Injection treatment. Withhold pemetrexed for acute onset of new or progressive unexplained pulmonary symptoms such as dyspnea, cough, or fever pending diagnostic evaluation.

If pneumonitis is confirmed, permanently discontinue Pemetrexed Injection.

5.5 Radiation Recall

Radiation recall can occur with Pemetrexed Injection in patients who have received radiation weeks to years previously. Monitor patients for inflammation or blistering in areas of previous radiation treatment. Permanently discontinue Pemetrexed Injection for signs of radiation recall.

5.6 Increased Risk of Toxicity with Ibuprofen in Patients with Renal Impairment

Exposure to pemetrexed is increased in patients with mild to moderate renal impairment who take concomitant ibuprofen, increasing the risks of adverse reactions of Pemetrexed Injection. In patients with creatinine clearances between 45 mL/min and 79 mL/min, avoid administration of ibuprofen for 2 days before, the day of, and 2 days following administration of Pemetrexed Injection.

If concomitant ibuprofen use cannot be avoided, monitor patients more frequently for pemetrexed adverse reactions, including myelosuppression, renal, and gastrointestinal toxicity [see Dosage and Administration (2.5), Drug Interactions (7), and Clinical Pharmacology (12.3)].

5.7 Embryo-Fetal Toxicity

Based on findings from animal studies and its mechanism of action, Pemetrexed Injection can cause fetal harm when administered to a pregnant woman. In animal reproduction studies, intravenous administration of pemetrexed to pregnant mice during the period of organogenesis was teratogenic, resulting in developmental delays and increased malformations at doses lower than the recommended human dose of 500 mg/m^2. Advise pregnant women of the potential risk to a fetus. Advise females of reproductive potential to use effective contraception during treatment with Pemetrexed Injection and for 6 months after the last dose. Advise males with female partners of reproductive potential to use effective contraception during treatment with Pemetrexed Injection and for 3 months after the last dose [see Use in Specific Populations (8.1, 8.3) and Clinical Pharmacology (12.1)].

6 ADVERSE REACTIONS

The following serious adverse reactions are described elsewhere in the labeling:

- Myelosuppression [see Warnings and Precautions (5.1)]
- Renal failure [see Warnings and Precautions (5.2)]
- Bullous and exfoliative skin toxicity [see Warning and Precautions (5.3)]
- Interstitial pneumonitis [see Warnings and Precautions (5.4)]
- Radiation recall [see Warnings and Precautions (5.5)]

6.1 Clinical Trials Experience

Because clinical trials are conducted under widely varying conditions, adverse reactions rates cannot be directly compared to rates in other clinical trials and may not reflect the rates observed in clinical practice.

In clinical trials, the most common adverse reactions (incidence ≥20%) of pemetrexed, when administered as a single agent, are fatigue, nausea, and anorexia. The most common adverse reactions (incidence ≥20%) of pemetrexed, when administered in combination with cisplatin are vomiting, neutropenia, anemia, stomatitis/pharyngitis, thrombocytopenia, and constipation. The most common adverse reactions (incidence ≥20%) of pemetrexed, when administered in combination with pembrolizumab and platinum chemotherapy, are fatigue/asthenia, nausea, constipation, diarrhea, decreased appetite, rash, vomiting, cough, dyspnea, and pyrexia.

Non-Squamous NSCLC

First-line Treatment of Metastatic Non-squamous NSCLC with Pembrolizumab and Platinum Chemotherapy

The safety of pemetrexed, in combination with pembrolizumab and investigator’s choice of platinum (either carboplatin or cisplatin), was investigated in Study KEYNOTE-189, a multicenter, double-blind, randomized (2:1), active-controlled trial in patients with previously untreated, metastatic non-squamous NSCLC with no EGFR or ALK genomic tumor aberrations. A total of 607 patients received pemetrexed, pembrolizumab, and platinum every 3 weeks for 4 cycles followed by pemetrexed and pembrolizumab (n=405), or placebo, pemetrexed, and platinum every 3 weeks for 4 cycles followed by placebo and pemetrexed (n=202). Patients with autoimmune disease that required systemic therapy within 2 years of treatment; a medical condition that required immunosuppression; or who had received more than 30 Gy of thoracic radiation within the prior 26 weeks were ineligible [see Clinical Studies (14.1)].

The median duration of exposure to pemetrexed was 7.2 months (range: 1 day to 1.7 years). Seventy-two percent of patients received carboplatin. The study population characteristics were: median age of 64 years (range: 34 to 84), 49% age 65 years or older, 59% male, 94% White and 3% Asian, and 18% with history of brain metastases at baseline.

Pemetrexed was discontinued for adverse reactions in 23% of patients in the pemetrexed, pembrolizumab, and platinum arm. The most common adverse reactions resulting in discontinuation of pemetrexed in this arm were acute kidney injury (3%) and pneumonitis (2%). Adverse reactions leading to interruption of pemetrexed occurred in 49% of patients in the pemetrexed, pembrolizumab, and platinum arm. The most common adverse reactions or laboratory abnormalities leading to interruption of pemetrexed in this arm (≥2%) were neutropenia (12%), anemia (7%), asthenia (4%), pneumonia (4%), thrombocytopenia (4%), increased blood creatinine (3%), diarrhea (3%), and fatigue (3%).

Table 2 summarizes the adverse reactions that occurred in ≥20% of patients treated with pemetrexed, pembrolizumab, and platinum.

Table 2: Adverse Reactions Occurring in ≥20% of Patients in KEYNOTE-189
 | Pemetrexed; Pembrolizumab; Platinum Chemotherapy; n=405 |  | Placebo; Pemetrexed; Platinum Chemotherapy; n=202
Adverse Reaction | All Gradesa; (%) | Grade 3-4 (%) | All Grades; (%) | Grade 3-4 (%)
Gastrointestinal Disorders
Nausea | 56 | 3.5 | 52 | 3.5
Constipation | 35 | 1.0 | 32 | 0.5
Diarrhea | 31 | 5 | 21 | 3.0
Vomiting | 24 | 3.7 | 23 | 3.0
General Disorders and Administration Site Conditions
Fatigueb | 56 | 12 | 58 | 6
Pyrexia | 20 | 0.2 | 15 | 0
Metabolism and Nutrition Disorders
Decreased appetite | 28 | 1.5 | 30 | 0.5
Skin and Subcutaneous Tissue Disorders
Rashc | 25 | 2.0 | 17 | 2.5
Respiratory, Thoracic and Mediastinal Disorders
Cough | 21 | 0 | 28 | 0
Dyspnea | 21 | 3.7 | 26 | 5
a Graded per NCI CTCAE version 4.03.
b Includes asthenia and fatigue.
c Includes genital rash, rash, rash generalized, rash macular, rash maculo-papular, rash papular, rash pruritic, and rash pustular.

Table 3 summarizes the laboratory abnormalities that worsened from baseline in at least 20% of patients treated with pemetrexed, pembrolizumab, and platinum.

Table 3: Laboratory Abnormalities Worsened from Baseline in ≥20% of Patients in KEYNOTE-189
 | Pemetrexed; Pembrolizumab; Platinum Chemotherapy |  | Placebo; Pemetrexed; Platinum Chemotherapy
Laboratory Testa | All Gradesb; % | Grades 3-4; % | All Grades; % | Grades 3-4; %
Chemistry
Hyperglycemia | 63 | 9 | 60 | 7
Increased ALT | 47 | 3.8 | 42 | 2.6
Increased AST | 47 | 2.8 | 40 | 1.0
Hypoalbuminemia | 39 | 2.8 | 39 | 1.1
Increased creatinine | 37 | 4.2 | 25 | 1.0
Hyponatremia | 32 | 7 | 23 | 6
Hypophosphatemia | 30 | 10 | 28 | 14
Increased alkaline phosphatase | 26 | 1.8 | 29 | 2.1
Hypocalcemia | 24 | 2.8 | 17 | 0.5
Hyperkalemia | 24 | 2.8 | 19 | 3.1
Hypokalemia | 21 | 5 | 20 | 5
Hematology
Anemia | 85 | 17 | 81 | 18
Lymphopenia | 64 | 22 | 64 | 25
Neutropenia | 48 | 20 | 41 | 19
Thrombocytopenia | 30 | 12 | 29 | 8
a Each test incidence is based on the number of patients who had both baseline and at least one on-study laboratory measurement available: Pemetrexed/pembrolizumab/platinum chemotherapy (range: 381 to 401 patients) and placebo/pemetrexed/platinum chemotherapy (range: 184 to 197 patients).
b Graded per NCI CTCAE version 4.03

Initial Treatment in Combination with Cisplatin

The safety of pemetrexed was evaluated in Study JMDB, a randomized (1:1), open-label, multicenter trial conducted in chemotherapy-naive patients with locally advanced or metastatic NSCLC. Patients received either pemetrexed 500 mg/m^2 intravenously and cisplatin 75 mg/m^2 intravenously on Day 1 of each 21-day cycle (n=839) or gemcitabine 1250 mg/m^2 intravenously on Days 1 and 8 and cisplatin 75 mg/m^2 intravenously on Day 1 of each 21-day cycle (n=830). All patients were fully supplemented with folic acid and vitamin B12.

Study JMDB excluded patients with an Eastern Cooperative Oncology Group Performance Status (ECOG PS of 2 or greater), uncontrolled third-space fluid retention, inadequate bone marrow reserve and organ function, or a calculated creatinine clearance less than 45 mL/min. Patients unable to stop using aspirin or other non-steroidal anti-inflammatory drugs or unable to take folic acid, vitamin B12 or corticosteroids were also excluded from the study.

The data described below reflect exposure to pemetrexed plus cisplatin in 839 patients in Study JMDB. Median age was 61 years (range 26-83 years); 70% of patients were men; 78% were White, 16% were Asian, 2.9% were Hispanic or Latino, 2.1% were Black or African American, and <1% were other ethnicities; 36% had an ECOG PS 0. Patients received a median of 5 cycles of pemetrexed.

Table 4 provides the frequency and severity of adverse reactions that occurred in ≥5% of 839 patients receiving pemetrexed in combination with cisplatin in Study JMDB. Study JMDB was not designed to demonstrate a statistically significant reduction in adverse reaction rates for pemetrexed, as compared to the control arm, for any specified adverse reaction listed in Table 4.

Table 4: Adverse Reactions Occurring in ≥5% of Fully Vitamin-Supplemented Patients Receiving Pemetrexed in Combination with Cisplatin Chemotherapy in Study JMDB
 | Pemetrexed/Cisplatin |  | Gemcitabine/Cisplatin
 | (N=839) |  | (N=830)
Adverse Reactiona | All Grades | Grade 3-4 | All Grades | Grade 3-4
 | (%) | (%) | (%) | (%)
All adverse reactions | 90 | 37 | 91 | 53
Laboratory
Hematologic
Anemia | 33 | 6 | 46 | 10
Neutropenia | 29 | 15 | 38 | 27
Thrombocytopenia | 10 | 4 | 27 | 13
Renal
Elevated creatinine | 10 | 1 | 7 | 1
Clinical
Constitutional symptoms
Fatigue | 43 | 7 | 45 | 5
Gastrointestinal
Nausea | 56 | 7 | 53 | 4
Vomiting | 40 | 6 | 36 | 6
Anorexia | 27 | 2 | 24 | 1
Constipation | 21 | 1 | 20 | 0
Stomatitis/pharyngitis | 14 | 1 | 12 | 0
Diarrhea | 12 | 1 | 13 | 2
Dyspepsia/heartburn | 5 | 0 | 6 | 0
Neurology
Sensory neuropathy | 9 | 0 | 12 | 1
Taste disturbance | 8 | 0 | 9 | 0
Dermatology/Skin
Alopecia | 12 | 0 | 21 | 1
Rash/Desquamation | 7 | 0 | 8 | 1
a NCI CTCAE version 2.0.

The following additional adverse reactions of pemetrexed were observed.

Incidence 1% to <5%

Body as a Whole — febrile neutropenia, infection, pyrexia

General Disorders — dehydration

Metabolism and Nutrition — increased AST, increased ALT

Renal —renal failure

Eye Disorder — conjunctivitis

Incidence <1%

Cardiovascular — arrhythmia

General Disorders — chest pain

Metabolism and Nutrition — increased GGT

Neurology — motor neuropathy

Maintenance Treatment Following First-line Non- Pemetrexed Containing Platinum-Based Chemotherapy

In Study JMEN, the safety of pemetrexed was evaluated in a randomized (2:1), placebo-controlled, multicenter trial conducted in patients with non-progressive locally advanced or metastatic NSCLC following four cycles of a first-line, platinum-based chemotherapy regimen. Patients received either pemetrexed 500 mg/m^2 or matching placebo intravenously every 21 days until disease progression or unacceptable toxicity. Patients in both study arms were fully supplemented with folic acid and vitamin B12.

Study JMEN excluded patients with an ECOG (Eastern Cooperative Oncology Group) performance status (PS) of 2 or greater, uncontrolled third-space fluid retention, inadequate bone marrow reserve and organ function, or a calculated creatinine clearance (CLcr) < 45 mL/min. Patients unable to stop using aspirin or other non-steroidal anti-inflammatory drugs (NSAIDS) or unable to take folic acid, vitamin B12 or corticosteroids were also excluded from the study.

The data described below reflect exposure to pemetrexed in 438 patients in Study JMEN. Median age was 61 years (range 26 to 83 years), 73% of patients were men; 65% were White, 31% were Asian, 2.9% were Hispanic or Latino, and <2% were other ethnicities; 39% had an ECOG PS 0. Patients received a median of 5 cycles of pemetrexed and a relative dose intensity of pemetrexed of 96%. Approximately half the patients (48%) completed at least six, 21-day cycles and 23% completed ten or more 21-day cycles of pemetrexed.

Table 5 provides the frequency and severity of adverse reactions reported in ≥5% of the 438 pemetrexed-treated patients in Study JMEN.

Table 5: Adverse Reactions Occurring in ≥5% of Patients Receiving Pemetrexed in Study JMEN
Adverse Reactiona | Pemetrexed; (N=438) |  | Placebo; (N=218)
Adverse Reactiona | All Grades; (%) | Grade 3-4; (%) | All Grades; (%) | Grade 3-4; (%)
All adverse reactions | 66 | 16 | 37 | 4
Laboratory
Hematologic
Anemia | 15 | 3 | 6 | 1
Neutropenia | 6 | 3 | 0 | 0
Hepatic
Increased ALT | 10 | 0 | 4 | 0
Increased AST | 8 | 0 | 4 | 0
Clinical
Constitutional symptoms
Fatigue | 25 | 5 | 11 | 1
Gastrointestinal
Nausea | 19 | 1 | 6 | 1
Anorexia | 19 | 2 | 5 | 0
Vomiting | 9 | 0 | 1 | 0
Mucositis/stomatitis | 7 | 1 | 2 | 0
Diarrhea | 5 | 1 | 3 | 0
Infection | 5 | 2 | 2 | 0
Neurology
Sensory neuropathy | 9 | 1 | 4 | 0
Dermatology/Skin
Rash/desquamation | 10 | 0 | 3 | 0
a NCI CTCAE version 3.0.

The requirement for transfusions (9.5% versus 3.2%), primarily red blood cell transfusions, and for erythropoiesis stimulating agents (5.9% versus 1.8%) were higher in the pemetrexed arm compared to the placebo arm.

The following additional adverse reactions were observed in patients who received pemetrexed.

Incidence 1% to<5%

Dermatology/Skin — alopecia, pruritus/itching

Gastrointestinal — constipation

General Disorders — edema, fever

Hematologic — thrombocytopenia

Eye Disorder — ocular surface disease (including conjunctivitis), increased lacrimation

Incidence <1%

Cardiovascular — supraventricular arrhythmia

Dermatology/Skin — erythema multiforme

General Disorders — febrile neutropenia, allergic reaction/hypersensitivity

Neurology — motor neuropathy

Renal — renal failure

Maintenance Treatment Following First-line Pemetrexed Plus Platinum Chemotherapy

The safety of pemetrexed was evaluated in PARAMOUNT, a randomized (2:1), placebo-controlled study conducted in patients with non-squamous NSCLC with non-progressive (stable or responding disease) locally advanced or metastatic NSCLC following four cycles of pemetrexed in combination with cisplatin as first-line therapy for NSCLC. Patients were randomized to receive pemetrexed 500 mg/m^2 or matching placebo intravenously on Day 1 of each 21-day cycle until disease progression or unacceptable toxicity. Patients in both study arms received folic acid and vitamin B12 supplementation.

PARAMOUNT excluded patients with an ECOG PS of 2 or greater, uncontrolled third-space fluid retention, inadequate bone marrow reserve and organ function, or a calculated creatinine clearance less than 45 mL/min. Patients unable to stop using aspirin or other non-steroidal anti-inflammatory drugs or unable to take folic acid, vitamin B12 or corticosteroids were also excluded from the study.

The data described below reflect exposure to pemetrexed in 333 patients in PARAMOUNT. Median age was 61 years (range 32 to 83 years); 58% of patients were men; 94% were White, 4.8% were Asian, and <1% were Black or African American; 36% had an ECOG PS 0. The median number of maintenance cycles was 4 for pemetrexed and placebo arms. Dose reductions for adverse reactions occurred in 3.3% of patients in the pemetrexed arm and 0.6% in the placebo arm. Dose delays for adverse reactions occurred in 22% of patients in the pemetrexed arm and 16% in the placebo arm.

Table 6 provides the frequency and severity of adverse reactions reported in ≥5% of the 333 pemetrexed-treated patients in PARAMOUNT.

Table 6: Adverse Reactions Occurring in ≥5% of Patients Receiving Pemetrexed in PARAMOUNT
Adverse Reactiona | Pemetrexed; (N=333) |  | Placebo; (N=167)
Adverse Reactiona | All Grades; (%) | Grade 3-4; (%) | All Grades; (%) | Grades 3-4; (%)
All adverse reactions | 53 | 17 | 34 | 4.8
Laboratory
Hematologic
Anemia | 15 | 4.8 | 4.8 | 0.6
Neutropenia | 9 | 3.9 | 0.6 | 0
Clinical
Constitutional symptoms
Fatigue | 18 | 4.5 | 11 | 0.6
Gastrointestinal
Nausea | 12 | 0.3 | 2.4 | 0
Vomiting | 6 | 0 | 1.8 | 0
Mucositis/stomatitis | 5 | 0.3 | 2.4 | 0
General disorders
Edema | 5 | 0 | 3.6 | 0
a NCI CTCAE version 3.0.

The requirement for red blood cell (13% versus 4.8%) and platelet (1.5% versus 0.6%) transfusions, erythropoiesis stimulating agents (12% versus 7%), and granulocyte colony stimulating factors (6% versus 0%) were higher in the pemetrexed arm compared to the placebo arm.

The following additional Grade 3 or 4 adverse reactions were observed more frequently in the pemetrexed arm.

Incidence 1% to <5%

Blood/Bone Marrow — thrombocytopenia

General Disorders — febrile neutropenia

Incidence <1%

Cardiovascular — ventricular tachycardia, syncope

General Disorders — pain

Gastrointestinal — gastrointestinal obstruction

Neurologic — depression

Renal — renal failure

Vascular — pulmonary embolism

Treatment of Recurrent Disease After Prior Chemotherapy

The safety of pemetrexed was evaluated in Study JMEI, a randomized (1:1), open-label, active-controlled trial conducted in patients who had progressed following platinum-based chemotherapy. Patients received pemetrexed 500 mg/m^2 intravenously or docetaxel 75 mg/m^2 intravenously on Day 1 of each 21-day cycle. All patients on the pemetrexed arm received folic acid and vitamin B12 supplementation.

Study JMEI excluded patients with an ECOG PS of 3 or greater, uncontrolled third-space fluid retention, inadequate bone marrow reserve and organ function, or a calculated creatinine clearance less than 45 mL/min. Patients unable to discontinue aspirin or other non-steroidal anti-inflammatory drugs or unable to take folic acid, vitamin B12 or corticosteroids were also excluded from the study.

The data described below reflect exposure to pemetrexed in 265 patients in Study JMEI. Median age was 58 years (range 22 to 87 years); 73% of patients were men; 70% were White, 24% were Asian, 2.6% were Black or African American, 1.8% were Hispanic or Latino, and <2% were other ethnicities; 19% had an ECOG PS 0.

Table 7 provides the frequency and severity of adverse reactions reported in ≥5% of the 265 pemetrexed-treated patients in Study JMEI. Study JMEI is not designed to demonstrate a statistically significant reduction in adverse reaction rates for pemetrexed, as compared to the control arm, for any specified adverse reaction listed in the Table 7 below.

Table 7: Adverse Reactions Occurring in ≥5% of Fully Supplemented Patients Receiving Pemetrexed in Study JMEI
Adverse Reactiona | Pemetrexed; (N=265) |  | Docetaxel; (N=276)
Adverse Reactiona | All Grades; (%) | Grades 3-4; (%) | All Grades; (%) | Grades 3-4; (%)
Laboratory
Hematologic
Anemia | 19 | 4 | 22 | 4
Neutropenia | 11 | 5 | 45 | 40
Thrombocytopenia | 8 | 2 | 1 | 0
Hepatic
Increased ALT | 8 | 2 | 1 | 0
Increased AST | 7 | 1 | 1 | 0
Clinical
Gastrointestinal
Nausea | 31 | 3 | 17 | 2
Anorexia | 22 | 2 | 24 | 3
Vomiting | 16 | 2 | 12 | 1
Stomatitis/pharyngitis | 15 | 1 | 17 | 1
Diarrhea | 13 | 0 | 24 | 3
Constipation | 6 | 0 | 4 | 0
Constitutional symptoms
Fatigue | 34 | 5 | 36 | 5
Fever | 8 | 0 | 8 | 0
Dermatology/Skin
Rash/desquamation | 14 | 0 | 6 | 0
Pruritus | 7 | 0 | 2 | 0
Alopecia | 6 | 1 | 38 | 2
a NCI CTCAE version 2.0.

The following additional adverse reactions were observed in patients assigned to receive pemetrexed.

Incidence 1% to <5%

Body as a Whole — abdominal pain, allergic reaction/hypersensitivity, febrile neutropenia, infection

Dermatology/Skin — erythema multiforme

Neurology — motor neuropathy, sensory neuropathy

Incidence <1%

Cardiovascular — supraventricular arrhythmias

Renal — renal failure

Mesothelioma

The safety of pemetrexed was evaluated in Study JMCH, a randomized (1:1), single-blind study conducted in patients with MPM who had received no prior chemotherapy for MPM. Patients received pemetrexed 500 mg/m^2 intravenously in combination with cisplatin 75 mg/m^2 intravenously on Day 1 of each 21-day cycle or cisplatin 75 mg/m^2 intravenously on Day 1 of each 21-day cycle administered until disease progression or unacceptable toxicity. Safety was assessed in 226 patients who received at least one dose of pemetrexed in combination with cisplatin and 222 patients who received at least one dose of cisplatin alone. Among 226 patients who received pemetrexed in combination with cisplatin, 74% (n=168) received full supplementation with folic acid and vitamin B12 during study therapy, 14% (n=32) were never supplemented, and 12% (n=26) were partially supplemented.

Study JMCH excluded patients with Karnofsky Performance Scale (KPS) of less than 70, inadequate bone marrow reserve and organ function, or a calculated creatinine clearance less than 45 mL/min. Patients unable to stop using aspirin or other non-steroidal anti-inflammatory drugs were also excluded from the study.

The data described below reflect exposure to pemetrexed in 168 patients that were fully supplemented with folic acid and vitamin B12. Median age was 60 years (range 19 to 85 years); 82% were men; 92% were White, 5% were Hispanic or Latino, 3.0% were Asian, and <1% were other ethnicities; 54% had KPS of 90 to 100. The median number of treatment cycles administered was 6 in the pemetrexed/cisplatin fully supplemented group and 2 in the pemetrexed/cisplatin never supplemented group. Patients receiving pemetrexed in the fully supplemented group had a relative dose intensity of 93% of the protocol-specified pemetrexed dose intensity. The most common adverse reaction resulting in dose delay was neutropenia.

Table 8 provides the frequency and severity of adverse reactions ≥5% in the subgroup of pemetrexed-treated patients who were fully vitamin supplemented in Study JMCH. Study JMCH was not designed to demonstrate a statistically significant reduction in adverse reaction rates for pemetrexed, as compared to the control arm, for any specified adverse reaction listed in the table below.

Table 8: Adverse Reactions Occurring in ≥5% of Fully Supplemented Subgroup of Patients Receiving Pemetrexed/Cisplatin in Study JMCHa
 | Pemetrexed/cisplatin |  | Cisplatin
 | (N=168) |  | (N=163)
Adverse Reactionb | All Grades | Grade 3-4 | All Grades | Grade 3-4
 | (%) | (%) | (%) | (%)
Laboratory
Hematologic
Neutropenia | 56 | 23 | 13 | 3
Anemia | 26 | 4 | 10 | 0
Thrombocytopenia | 23 | 5 | 9 | 0
Renal
Elevated creatinine | 11 | 1 | 10 | 1
Decreased creatinine clearance | 16 | 1 | 18 | 2
Clinical
Eye Disorder
Conjunctivitis | 5 | 0 | 1 | 0
Gastrointestinal
Nausea | 82 | 12 | 77 | 6
Vomiting | 57 | 11 | 50 | 4
Stomatitis/pharyngitis | 23 | 3 | 6 | 0
Anorexia | 20 | 1 | 14 | 1
Diarrhea | 17 | 4 | 8 | 0
Constipation | 12 | 1 | 7 | 1
Dyspepsia | 5 | 1 | 1 | 0
Constitutional Symptoms
Fatigue | 48 | 10 | 42 | 9
Metabolism and Nutrition
Dehydration | 7 | 4 | 1 | 1
Neurology
Sensory neuropathy | 10 | 0 | 10 | 1
Taste disturbance | 8 | 0 | 6 | 0
Dermatology/Skin
Rash | 16 | 1 | 5 | 0
Alopecia | 11 | 0 | 6 | 0
a In Study JMCH, 226 patients received at least one dose of pemetrexed in combination with cisplatin and 222 patients received at least one dose of cisplatin. Table 8 provides the ADRs for subgroup of patients treated with pemetrexed in combination with cisplatin (168 patients) or cisplatin alone (163 patients) who received full supplementation with folic acid and vitamin B12 during study therapy.
b NCI CTCAE version 2.0.

The following additional adverse reactions were observed in patients receiving pemetrexed plus cisplatin:

Incidence 1% to <5%

Body as a Whole — febrile neutropenia, infection, pyrexia

Dermatology/Skin — urticaria

General Disorders — chest pain

Metabolism and Nutrition — increased AST, increased ALT, increased GGT

Renal — renal failure

Incidence <1%

Cardiovascular — arrhythmia

Neurology — motor neuropathy

Exploratory Subgroup Analyses based on Vitamin Supplementation

Table 9 provides the results of exploratory analyses of the frequency and severity of NCI CTCAE Grade 3 or 4 adverse reactions reported in more pemetrexed-treated patients who did not receive vitamin supplementation (never supplemented) as compared with those who received vitamin supplementation with daily folic acid and vitamin B12 from the time of enrollment in Study JMCH (fully-supplemented).

Table 9: Exploratory Subgroup Analysis of Selected Grade 3/4 Adverse Reactions Occurring in Patients Receiving Pemetrexed in Combination with Cisplatin with or without Full Vitamin Supplementation in Study JMCHa
 | Fully Supplemented | Never Supplemented
 | Patients | Patients
 | N=168 | N=32
Grade 3-4 Adverse Reactions | (%) | (%)
Neutropenia | 23 | 38
Thrombocytopenia | 5 | 9
Vomiting | 11 | 31
Febrile neutropenia | 1 | 9
Infection with Grade 3/4 neutropenia | 0 | 6
Diarrhea | 4 | 9
a NCI CTCAE version 2.0

The following adverse reactions occurred more frequently in patients who were fully vitamin supplemented than in patients who were never supplemented:

- hypertension (11% versus 3%),
- chest pain (8% versus 6%),
- thrombosis/embolism (6% versus 3%).

Additional Experience Across Clinical Trials

Sepsis, with or without neutropenia, including fatal cases: 1%

Severe esophagitis, resulting in hospitalization: <1%

6.2 Postmarketing Experience

The following adverse reactions have been identified during post-approval use of pemetrexed. Because these reactions are reported voluntarily from a population of uncertain size, it is not always possible to reliably estimate their frequency or establish a causal relationship to drug exposure.

Blood and Lymphatic System — immune-mediated hemolytic anemia

Gastrointestinal — colitis, pancreatitis

General Disorders and Administration Site Conditions — edema

Injury, poisoning, and procedural complications — radiation recall

Respiratory — interstitial pneumonitis

Skin — Serious and fatal bullous skin conditions, Stevens-Johnson syndrome, and toxic epidermal necrolysis

7 DRUG INTERACTIONS

Effects of Ibuprofen on Pemetrexed

Ibuprofen increases exposure (AUC) of pemetrexed [see Clinical Pharmacology (12.3)]. In patients with creatinine clearance between 45 mL/min and 79 mL/min:

- Avoid administration of ibuprofen for 2 days before, the day of, and 2 days following administration of Pemetrexed Injection [see Dosage and Administration (2.5)].
- Monitor patients more frequently for myelosuppression, renal, and gastrointestinal toxicity, if concomitant administration of ibuprofen cannot be avoided.

8 USE IN SPECIFIC POPULATIONS

8.1 Pregnancy

Risk Summary

Based on findings from animal studies and its mechanism of action, Pemetrexed Injection can cause fetal harm when administered to a pregnant woman [see Clinical Pharmacology (12.1)]. There are no available data on Pemetrexed Injection use in pregnant women. In animal reproduction studies, intravenous administration of pemetrexed to pregnant mice during the period of organogenesis was teratogenic, resulting in developmental delays and malformations at doses lower than the recommended human dose of 500 mg/m^2 [see Data]. Advise pregnant women of the potential risk to a fetus [see Use in Special Populations (8.3)].

In the U.S. general population, the estimated background risk of major birth defects and miscarriage in clinically recognized pregnancies is 2 to 4% and 15 to 20%, respectively.

Data

Animal Data

Pemetrexed was teratogenic in mice. Daily dosing of pemetrexed by intravenous injection to pregnant mice during the period of organogenesis increased the incidence of fetal malformations (cleft palate; protruding tongue; enlarged or misshaped kidney; and fused lumbar vertebra) at doses (based on BSA) 0.03 times the human dose of 500 mg/m^2. At doses, based on BSA, greater than or equal to 0.0012 times the 500 mg/m^2 human dose, pemetrexed administration resulted in dose-dependent increases in developmental delays (incomplete ossification of talus and skull bone; and decreased fetal weight).

8.2 Lactation

Risk Summary

There is no information regarding the presence of pemetrexed or its metabolites in human milk, the effects on the breastfed child, or the effects on milk production. Because of the potential for serious adverse reactions in breastfed children from Pemetrexed Injection, advise women not to breastfeed during treatment with Pemetrexed Injection and for one week after the last dose.

8.3 Females and Males of Reproductive Potential

Based on animal data, Pemetrexed Injection can cause malformations and developmental delays when administered to a pregnant woman [see Use in Specific Populations (8.1)].

Pregnancy Testing

Verify pregnancy status of females of reproductive potential prior to initiating Pemetrexed Injection [see Use in Specific Populations (8.1)].

Contraception

Females

Because of the potential for genotoxicity, advise females of reproductive potential to use effective contraception during treatment with Pemetrexed Injection and for 6 months after the last dose.

Males

Because of the potential for genotoxicity, advise males with female partners of reproductive potential to use effective contraception during treatment with Pemetrexed Injection and for 3 months after the last dose [see Nonclinical Toxicology (13.1)].

Infertility

Males

Pemetrexed Injection may impair fertility in males of reproductive potential. It is not known whether these effects on fertility are reversible [see Nonclinical Toxicology (13.1)].

8.4 Pediatric Use

The safety and effectiveness of pemetrexed in pediatric patients have not been established.

The safety and pharmacokinetics of pemetrexed were evaluated in two clinical studies conducted in pediatric patients with recurrent solid tumors (NCT00070473, N=32 and NCT00520936, N=72). Patients in both studies received concomitant vitamin B12 and folic acid supplementation and dexamethasone.

No tumor responses were observed. Adverse reactions observed in pediatric patients were similar to those observed in adults.

Pharmacokinetics of pemetrexed in 22 patients age 4 to 18 years enrolled in NCT00070473 were within range of values in adults.

8.5 Geriatric Use

Of the 3,946 patients enrolled in clinical studies of pemetrexed, 34% were 65 and over and 4% were 75 and over. No overall differences in effectiveness were observed between these patients and younger patients. The incidences of Grade 3-4 anemia, fatigue, thrombocytopenia, hypertension, and neutropenia were higher in patients 65 years of age and older as compared to younger patients in at least one of five randomized clinical trials [see Adverse Reactions (6.1) and Clinical Studies (14.1, 14.2)].

8.6 Patients with Renal Impairment

Pemetrexed is primarily excreted by the kidneys. Decreased renal function results in reduced clearance and greater exposure (AUC) to pemetrexed compared with patients with normal renal function [Warnings and Precautions (5.2, 5.6) and Clinical Pharmacology (12.3)]. No dose is recommended for patients with creatinine clearance less than 45 mL/min [see Dosage and Administration (2.3)].

10 OVERDOSAGE

No drugs are approved for the treatment of Pemetrexed Injection overdose. Based on animal studies, administration of leucovorin may mitigate the toxicities of Pemetrexed Injection overdosage. It is not known whether pemetrexed is dialyzable.

11 DESCRIPTION

Pemetrexed is a folate analog metabolic inhibitor. The drug substance, pemetrexed diacid monohydrate, has the chemical name N-[4-[2-(2-amino-4,7-dihydro-4-oxo-1H-pyrrolo[2,3-d] pyrimidin-5-yl)ethyl]benzoyl]-L-glutamic acid, monohydrate with a molecular formula of C20H21N5O6 • H2O and a molecular weight of 445.43. It is practically insoluble in water. The structural formula is as follows:

Pemetrexed Injection is supplied as a sterile solution for intravenous infusion available in single-dose vials. The product is a clear to slightly yellowish or slightly yellow-greenish solution. Each mL contains 25 mg pemetrexed, 35 mg tromethamine, 10 mg citric acid anhydrous, 0.5 mg methionine and water for injection. Tromethamine may have been added to adjust pH.

12 CLINICAL PHARMACOLOGY

12.1 Mechanism of Action

Pemetrexed Injection is a folate analog metabolic inhibitor that disrupts folate-dependent metabolic processes essential for cell replication. In vitro studies show that pemetrexed inhibits thymidylate synthase (TS), dihydrofolate reductase, and glycinamide ribonucleotide formyltransferase (GARFT), which are folate-dependent enzymes involved in the de novo biosynthesis of thymidine and purine nucleotides. Pemetrexed is taken into cells by membrane carriers such as the reduced folate carrier and membrane folate binding protein transport systems. Once in the cell, pemetrexed is converted to polyglutamate forms by the enzyme folylpolyglutamate synthetase. The polyglutamate forms are retained in cells and are inhibitors of TS and GARFT.

12.2 Pharmacodynamics

Pemetrexed inhibited the in vitro growth of mesothelioma cell lines (MSTO-211H, NCI-H2052) and showed synergistic effects when combined with cisplatin.

Based on population pharmacodynamic analyses, the depth of the absolute neutrophil counts (ANC) nadir correlates with the systemic exposure to pemetrexed and supplementation with folic acid and vitamin B12. There is no cumulative effect of pemetrexed exposure on ANC nadir over multiple treatment cycles.

12.3 Pharmacokinetics

The pharmacokinetics of pemetrexed when pemetrexed was administered as a single agent in doses ranging from 0.2 to 838 mg/m^2 [0.0004 to 1.7 times the recommended dosage] infused over a 10-minute period have been evaluated in 426 cancer patients with a variety of solid tumors. Pemetrexed total systemic exposure (AUC) and maximum plasma concentration (Cmax) increased proportionally with increase of dose. The pharmacokinetics of pemetrexed did not change over multiple treatment cycles.

Distribution

Pemetrexed has a steady-state volume of distribution of 16.1 liters. In vitro studies indicated that pemetrexed is 81% bound to plasma proteins.

Elimination

The total systemic clearance of pemetrexed is 91.8 mL/min and the elimination half-life of pemetrexed is 3.5 hours in patients with normal renal function (creatinine clearance of 90 mL/min). As renal function decreases, the clearance of pemetrexed decreases and exposure (AUC) of pemetrexed increases.

Metabolism

Pemetrexed is not metabolized to an appreciable extent.

Excretion

Pemetrexed is primarily eliminated in the urine, with 70% to 90% of the dose recovered unchanged within the first 24 hours following administration. In vitro studies indicated that pemetrexed is a substrate of OAT3 (organic anion transporter 3), a transporter that is involved in the active secretion of pemetrexed.

Specific Populations

Age (26 to 80 years) and sex had no clinically meaningful effect on the systemic exposure of pemetrexed based on population pharmacokinetic analyses.

Racial Groups

The pharmacokinetics of pemetrexed were similar in Whites and Blacks or African Americans. Insufficient data are available for other ethnic groups.

Patients with Hepatic Impairment

Pemetrexed has not been formally studied in patients with hepatic impairment. No effect of elevated AST, ALT, or total bilirubin on the PK of pemetrexed was observed in clinical studies.

Patients with Renal Impairment

Pharmacokinetic analyses of pemetrexed included 127 patients with impaired renal function. Plasma clearance of pemetrexed decreases as renal function decreases, with a resultant increase in systemic exposure. Patients with creatinine clearances of 45, 50, and 80 mL/min had 65%, 54%, and 13% increases, respectively in systemic exposure (AUC) compared to patients with creatinine clearance of 100 mL/min [see Dosage and Administration (2.3) and Warnings and Precautions (5.2)].

Third-Space Fluid

The pemetrexed plasma concentrations in patients with various solid tumors with stable, mild to moderate
third-space fluid were comparable to those observed in patients without third space fluid collections. The effect of severe third space fluid on pharmacokinetics is not known.

Drug Interaction Studies

Drugs Inhibiting OAT3 Transporter

Ibuprofen, an OAT3 inhibitor, administered at 400 mg four times a day decreased the clearance of pemetrexed and increased its exposure (AUC) by approximately 20% in patients with normal renal function (creatinine clearance >80 mL/min).

In Vitro Studies

Pemetrexed is a substrate for OAT3. Ibuprofen, an OAT3 inhibitor inhibited the uptake of pemetrexed in OAT3-expressing cell cultures with an average [Iu]/IC50 ratio of 0.38. In vitro data predict that at clinically relevant concentrations, other NSAIDs (naproxen, diclofenac, celecoxib) would not inhibit the uptake of pemetrexed by OAT3 and would not increase the AUC of pemetrexed to a clinically significant extent [see Drug Interactions (7)].

Pemetrexed is a substrate for OAT4. In vitro, ibuprofen and other NSAIDs (naproxen, diclofenac, celecoxib) are not inhibitors of OAT4 at clinically relevant concentrations.

Aspirin

Aspirin, administered in low to moderate doses (325 mg every 6 hours), does not affect the pharmacokinetics of pemetrexed.

Cisplatin

Cisplatin does not affect the pharmacokinetics of pemetrexed and the pharmacokinetics of total platinum are unaltered by pemetrexed.

Vitamins

Neither folic acid nor vitamin B12 affect the pharmacokinetics of pemetrexed.

Drugs Metabolized by Cytochrome P450 Enzymes

In vitro studies suggest that pemetrexed does not inhibit the clearance of drugs metabolized by CYP3A, CYP2D6, CYP2C9, and CYP1A2.

13 NONCLINICAL TOXICOLOGY

13.1 Carcinogenesis, Mutagenesis, Impairment of Fertility

No carcinogenicity studies have been conducted with pemetrexed. Pemetrexed was clastogenic in an in vivo micronucleus assay in mouse bone marrow but was not mutagenic in multiple in vitro tests (Ames assay, Chinese Hamster Ovary cell assay).

Pemetrexed administered intraperitoneally at doses of ≥0.1 mg/kg/day to male mice (approximately 0.0006 times the recommended human dose based on BSA) resulted in reduced fertility, hypospermia, and testicular atrophy.

14 CLINICAL STUDIES

14.1 Non-Squamous NSCLC

Initial Treatment in Combination with Pembrolizumab and Platinum

The efficacy of pemetrexed in combination with pembrolizumab and platinum chemotherapy was investigated in Study KEYNOTE-189 (NCT02578680), a randomized, multicenter, double-blind, active-controlled trial conducted in patients with metastatic non-squamous NSCLC, regardless of PD-L1 tumor expression status, who had not previously received systemic therapy for metastatic disease and in whom there were no EGFR or ALK genomic tumor aberrations. Patients with autoimmune disease that required systemic therapy within 2 years of treatment; a medical condition that required immunosuppression; or who had received more than 30 Gy of thoracic radiation within the prior 26 weeks were ineligible. Randomization was stratified by smoking status (never versus former/current), choice of platinum (cisplatin versus carboplatin), and tumor PD-L1 status (TPS <1% [negative] versus TPS ≥1%). Patients were randomized (2:1) to one of the following treatment arms:

- Pemetrexed 500 mg/m^2, pembrolizumab 200 mg, and investigator’s choice of cisplatin 75 mg/m^2 or carboplatin AUC 5 mg/mL/min intravenously on Day 1 of each 21-day cycle for 4 cycles followed by pemetrexed 500 mg/m^2 and pembrolizumab 200 mg intravenously every 3 weeks. Pemetrexed was administered after pembrolizumab and prior to platinum chemotherapy on Day 1.
- Placebo, pemetrexed 500 mg/m^2, and investigator’s choice of cisplatin 75 mg/m^2 or carboplatin AUC 5 mg/mL/min intravenously on Day 1 of each 21-day cycle for 4 cycles followed by placebo and pemetrexed 500 mg/m^2 intravenously every 3 weeks.

Treatment with pemetrexed continued until RECIST v1.1 (modified to follow a maximum of 10 target lesions and a maximum of 5 target lesions per organ)-defined progression of disease as determined by the investigator or unacceptable toxicity. Patients randomized to placebo, pemetrexed, and platinum chemotherapy were offered pembrolizumab as a single agent at the time of disease progression.

Assessment of tumor status was performed at Week 6, Week 12, and then every 9 weeks thereafter. The main efficacy outcome measures were OS and PFS as assessed by BICR RECIST v1.1, modified to follow a maximum of 10 target lesions and a maximum of five target lesions per organ. Additional efficacy outcome measures were ORR and duration of response, as assessed by the BICR according to RECIST v1.1, modified to follow a maximum of 10 target lesions and a maximum of 5 target lesions per organ.

A total of 616 patients were randomized: 410 patients to the pemetrexed, pembrolizumab, and platinum chemotherapy arm and 206 to the placebo, pemetrexed, and platinum chemotherapy arm. The study population characteristics were: median age of 64 years (range: 34 to 84); 49% age 65 or older; 59% male; 94% White and 3% Asian; 56% ECOG performance status of 1; and 18% with history of brain metastases. Thirty-one percent had tumor PD-L1 expression TPS <1%. Seventy-two percent received carboplatin and 12% were never smokers. A total of 85 patients in the placebo, pemetrexed, and chemotherapy arm received an anti-PD-1/PD-L1 monoclonal antibody at the time of disease progression.

The trial demonstrated a statistically significant improvement in OS and PFS for patients randomized to pemetrexed in combination with pembrolizumab and platinum chemotherapy compared with placebo, pemetrexed, and platinum chemotherapy (see Table 10 and Figure 1).

Table 10: Efficacy Results of KEYNOTE-189
Endpoint | Pemetrexed; Pembrolizumab; Platinum Chemotherapy; n=410 | Placebo; Pemetrexed; Platinum Chemotherapy; n=206
OS
Number (%) of patients with event | 127 (31%) | 108 (52%)
Median in months (95% CI) | NR (NR, NR) | 11.3 (8.7, 15.1)
Hazard ratioa (95% CI) | 0.49 (0.38, 0.64)
p-valueb | <0.0001
PFS
Number of patients with event (%) | 245 (60%) | 166 (81%)
Median in months (95% CI) | 8.8 (7.6, 9.2) | 4.9 (4.7, 5.5)
Hazard ratioa (95% CI) | 0.52 (0.43, 0.64)
p-valueb | <0.0001
ORR
Overall response ratec (95% CI) | 48% (43, 53) | 19% (14, 25)
Complete response | 0.5% | 0.5%
Partial response | 47% | 18%
p-valued | <0.0001
Duration of Response
Median in months (range) | 11.2 (1.1+, 18.0+) | 7.8 (2.1+, 16.4+)
a Based on the stratified Cox proportional hazard model.
b Based on stratified log-rank test.
c Response: Best objective response as confirmed complete response or partial response.
d Based on Miettinen and Nurminen method stratified by PD-L1 status, platinum chemotherapy and smoking status. NR = not reached

At the protocol specified final OS analysis, the median in the pemetrexed in combination with pembrolizumab and platinum chemotherapy arm was 22.0 months (95% CI: 19.5, 24.5) compared to 10.6 months (95% CI: 8.7, 13.6) in the placebo with pemetrexed and platinum chemotherapy arm, with an HR of 0.56 (95% CI: 0.46, 0.69).

Pemetrexed +P+C = Pemetrexed + pembrolizumab + platinum chemotherapy.

Pemetrexed +C = Pemetrexed + platinum chemotherapy + placebo

Figure 1: Kaplan-Meier Curve for Overall Survival in KEYNOTE-189*

*Based on the protocol-specified final OS analysis

Initial Treatment in Combination with Cisplatin

The efficacy of pemetrexed was evaluated in Study JMDB (NCT00087711), a multi-center, randomized (1:1), open-label study conducted in 1725 chemotherapy-naive patients with Stage IIIb/IV NSCLC. Patients were randomized to receive pemetrexed with cisplatin or gemcitabine with cisplatin. Randomization was stratified by Eastern Cooperative Oncology Group Performance Status (ECOG PS 0 versus 1), gender, disease stage, basis for pathological diagnosis (histopathological/cytopathological), history of brain metastases, and investigative center. Pemetrexed was administered intravenously over 10 minutes at a dose of 500 mg/m^2 on Day 1 of each 21-day cycle. Cisplatin was administered intravenously at a dose of 75 mg/m^2 approximately 30 minutes after pemetrexed administration on Day 1 of each cycle, gemcitabine was administered at a dose of 1250 mg/m^2 on Day 1 and Day 8, and cisplatin was administered intravenously at a dose of 75 mg/m^2 approximately 30 minutes after administration of gemcitabine, on Day 1 of each 21-day cycle. Treatment was administered up to a total of 6 cycles; patients in both arms received folic acid, vitamin B12, and dexamethasone [see Dosage and Administration (2.4)]. The primary efficacy outcome measure was overall survival.

A total of 1725 patients were enrolled with 862 patients randomized to pemetrexed in combination with cisplatin and 863 patients to gemcitabine in combination with cisplatin. The median age was 61 years (range 26-83 years), 70% were male, 78% were White, 17% were Asian, 2.9% were Hispanic or Latino, and 2.1% were Black or African American, and <1% were other ethnicities. Among patients for whom ECOG PS (n=1722) and smoking history (n=1516) were collected, 65% had an ECOG PS of 1, 36% had an ECOG PS of 0, and 84% were smokers. For tumor characteristics, 73% had non-squamous NSCLC and 27% had squamous NSCLC; 76% had Stage IV disease. Among 1252 patients with non- squamous NSCLC histology, 68% had a diagnosis of adenocarcinoma, 12% had large cell histology and 20% had other histologic subtypes.

Efficacy results in Study JMDB are presented in Table 11 and Figure 2.

Table 11: Efficacy Results in Study JMDB
Efficacy Parameter | Pemetrexed plus Cisplatin; (N=862) | Gemcitabine plus Cisplatin; (N=863)
Overall Survival
Median (months) | 10.3 | 10.3
(95% CI) | (9.8 to 11.2) | (9.6 to 10.9)
Hazard ratio (HR)a,b | 0.94
(95% CI) | (0.84-1.05)
Progression-Free Survival
Median (months) | 4.8 | 5.1
(95% CI) | (4.6 to 5.3) | (4.6 to 5.5)
Hazard ratio (HR)a,b | 1.04
(95% CI) | (0.94-1.15)
Overall Response Rate | 27.1% | 24.7%
(95% CI) | (24.2 to 30.1) | (21.8 to 27.6)
a Unadjusted for multiple comparisons.
b Adjusted for gender, stage, basis of diagnosis, and performance status.

Figure 2: Kaplan-Meier Curves for Overall Survival in Study JMDB

In pre-specified analyses assessing the impact of NSCLC histology on overall survival, clinically relevant differences in survival according to histology were observed. These subgroup analyses are shown in Table 12 and Figures 3 and 4. This difference in treatment effect for pemetrexed based on histology demonstrating a lack of efficacy in squamous cell histology was also observed in Studies JMEN and JMEI.

Table 12: Overall Survival in NSCLC Histologic Subgroups in Study JMDB
Histologic Subgroups | Pemetrexed plus; Cisplatin; (N=862) | Gemcitabine plus Cisplatin; (N=863)
Non-squamous NSCLC (N=1252)
Median (months) | 11.0 | 10.1
(95% CI) | (10.1 to 12.5) | (9.3 to 10.9)
HRa,b | 0.84
(95% CI) | (0.74 to 0.96)
Adenocarcinoma (N=847)
Median (months) | 12.6 | 10.9
(95% CI) | (10.7 to 13.6) | (10.2 to 11.9)
HRa,b | 0.84
(95% CI) | (0.71 to 0.99)
Large Cell (N=153)
Median (months) | 10.4 | 6.7
(95% CI) | (8.6 to 14.1) | (5.5 to 9.0)
HRa,b | 0.67
(95% CI) | (0.48 to 0.96)
Non-squamous, not otherwise specified (N=252)
Median (months) | 8.6 | 9.2
(95% CI) | (6.8 to 10.2) | (8.1 to 10.6)
HRa,b | 1.08
(95% CI) | (0.81 to 1.45)
Squamous Cell (N=473)
Median (months) | 9.4 | 10.8
(95% CI) | (8.4 to 10.2) | (9.5 to 12.1)
HRa,b | 1.23
(95% CI) | (1.00 to 1.51)
a Unadjusted for multiple comparisons.
b Adjusted for ECOG PS, gender, disease stage, and basis for pathological diagnosis (histopathological/cytopathological).

Figure 3: Kaplan-Meier Curves for Overall Survival in Non-squamous NSCLC in Study JMDB

Figure 4: Kaplan-Meier Curves for Overall Survival in Squamous NSCLC in Study JMDB

Maintenance Treatment Following First-line Non-Pemetrexed Containing Platinum-Based Chemotherapy

The efficacy of pemetrexed as maintenance therapy following first-line platinum-based chemotherapy was evaluated in Study JMEN (NCT00102804), a multicenter, randomized (2:1), double-blind, placebo-controlled study conducted in 663 patients with Stage IIIb/IV NSCLC who did not progress after four cycles of platinum-based chemotherapy. Patients were randomized to receive pemetrexed 500 mg/m^2 intravenously every 21 days or placebo until disease progression or intolerable toxicity. Patients in both study arms received folic acid, vitamin B12, and dexamethasone [see Dosage and Administration (2.4)]. Randomization was carried out using a minimization approach [Pocock and Simon (1975)] using the following factors: gender, ECOG PS (0 versus 1), response to prior chemotherapy (complete or partial response versus stable disease), history of brain metastases (yes versus no), non-platinum component of induction therapy (docetaxel versus gemcitabine versus paclitaxel), and disease stage (IIIb versus IV). The major efficacy outcome measures were progression-free survival based on assessment by independent review and overall survival; both were measured from the date of randomization in Study JMEN.

A total of 663 patients were enrolled with 441 patients randomized to pemetrexed and 222 patients randomized to placebo. The median age was 61 years (range 26-83 years); 73% were male; 65% were White, 32% were Asian, 2.9% were Hispanic or Latino, and <2% were other ethnicities; 60% had an ECOG PS of 1; and 73% were current or former smokers. Median time from initiation of platinum-based chemotherapy to randomization was 3.3 months (range 1.6 to 5.1 months) and 49% of the population achieved a partial or complete response to first-line, platinum-based chemotherapy. With regard to tumor characteristics, 81% had Stage IV disease, 73% had non-squamous NSCLC and 27% had squamous NSCLC. Among the 481 patients with non-squamous NSCLC, 68% had adenocarcinoma, 4% had large cell, and 28% had other histologies.

Efficacy results are presented in Table 13 and Figure 5.

Table 13: Efficacy Results in Study JMEN
Efficacy Parameter | Pemetrexed | Placebo
Overall survival | N=441 | N=222
Median (months) | 13.4 | 10.6
(95% CI) | (11.9-15.9) | (8.7-12.0)
Hazard ratioa | 0.79
(95% CI) | (0.65-0.95)
p-value | p=0.012
Progression-free survival per independent review | N=387 | N=194
Median (months) | 4.0 | 2.0
(95% CI) | (3.1-4.4) | (1.5-2.8)
Hazard ratioa | 0.60
(95% CI) | (0.49-0.73)
p-value | p<0.00001
a Hazard ratios are adjusted for multiplicity but not for stratification variables.

Figure 5: Kaplan-Meier Curves for Overall Survival in Study JMEN

The results of pre-specified subgroup analyses by NSCLC histology are presented in Table 14 and Figures 6 and 7.

Table 14: Efficacy Results in Study JMEN by Histologic Subgroup
Efficacy Parameter | Overall Survival |  | Progression-Free Survival; Per Independent Review
Efficacy Parameter | Pemetrexed; (N=441) | Placebo; (N=222) | Pemetrexed; (N=387) | Placebo; (N=194)
Non-squamous NSCLC (n=481)
Median (months) | 15.5 | 10.3 | 4.4 | 1.8
HRa | 0.70 |  | 0.47
(95% CI) | (0.56 to 0.88) |  | (0.37 to 0.60)
Adenocarcinoma (n=328)
Median (months) | 16.8 | 11.5 | 4.6 | 2.7
HRa | 0.73 |  | 0.51
(95% CI) | (0.56 to 0.96) |  | (0.38 to 0.68)
Large cell carcinoma (n=20)
Median (months) | 8.4 | 7.9 | 4.5 | 1.5
HRa | 0.98 |  | 0.40
(95% CI) | (0.36 to 2.65) |  | (0.12 to 1.29)
Otherb (n=133)
Median (months) | 11.3 | 7.7 | 4.1 | 1.6
HRa | 0.61 |  | 0.44
(95% CI) | (0.40 to 0.94) |  | (0.28 to 0.68)
Squamous cell NSCLC (n=182)
Median (months) | 9.9 | 10.8 | 2.4 | 2.5
HRa | 1.07 |  | 1.03
(95% CI) | (0.77 to 1.50) |  | (0.71 to 1.49)
a Hazard ratios are not adjusted for multiplicity
b Primary diagnosis of NSCLC not specified as adenocarcinoma, large cell carcinoma, or squamous cell carcinoma.

Figure 6: Kaplan-Meier Curves for Overall Survival in Non-squamous NSCLC in Study JMEN

Figure 7: Kaplan-Meier Curves for Overall Survival in Squamous NSCLC in Study JMEN

Maintenance Treatment Following First-line Pemetrexed Plus Platinum Chemotherapy

The efficacy of pemetrexed as maintenance therapy following first-line platinum-based chemotherapy was also evaluated in PARAMOUNT (NCT00789373), a multi-center, randomized (2:1), double-blind, placebo-controlled study conducted in patients with Stage IIIb/IV non-squamous NSCLC who had completed four cycles of pemetrexed in combination with cisplatin and achieved a complete response (CR) or partial response (PR) or stable disease (SD). Patients were required to have an ECOG PS of 0 or 1. Patients were randomized to receive pemetrexed 500 mg/m^2 intravenously every 21 days or placebo until disease progression. Randomization was stratified by response to pemetrexed in combination with cisplatin induction therapy (CR or PR versus SD), disease stage (IIIb versus IV), and ECOG PS (0 versus 1). Patients in both arms received folic acid, vitamin B12, and dexamethasone. The main efficacy outcome measure was investigator-assessed progression- free survival (PFS) and an additional efficacy outcome measure was overall survival (OS); PFS and OS were measured from the time of randomization.

A total of 539 patients were enrolled with 359 patients randomized to pemetrexed and 180 patients randomized to placebo. The median age was 61 years (range 32 to 83 years); 58% were male; 95% were White, 4.5% were Asian, and <1% were Black or African American; 67% had an ECOG PS of 1; 78% were current or former smokers; and 43% of the population achieved a partial or complete response to first-line, platinum-based chemotherapy. With regard to tumor characteristics, 91% had Stage IV disease, 87% had adenocarcinoma, 7% had large cell, and 6% had other histologies.

Efficacy results for PARAMOUNT are presented in Table 15 and Figure 8.

Table 15: Efficacy Results in PARAMOUNT
Efficacy Parameter | Pemetrexed (N=359) | Placebo; (N=180)
Overall survival
Median (months) | 13.9 | 11.0
(95% CI) | (12.8 to 16.0) | (10.0 to 12.5)
Hazard ratio (HR)a | 0.78
(95% CI) | (0.64 to 0.96)
p-value | p=0.02
Progression-free survivalb
Median (months) | 4.1 | 2.8
(95% CI) | (3.2 to 4.6) | (2.6 to 3.1)
Hazard ratio (HR)a | 0.62
(95% CI) | (0.49 to 0.79)
p-value | p<0.0001
a Hazard ratios are adjusted for multiplicity but not for stratification variables.
b Based on investigator’s assessment.

Figure 8: Kaplan-Meier Curves for Overall Survival in PARAMOUNT

Treatment of Recurrent Disease After Prior Chemotherapy

The efficacy of pemetrexed was evaluated in Study JMEI (NCT00004881), a multicenter, randomized (1:1), open-label study conducted in patients with Stage III or IV NSCLC that had recurred or progressed following one prior chemotherapy regimen for advanced disease. Patients were randomized to receive pemetrexed 500 mg/m^2 intravenously or docetaxel 75 mg/m^2 as a 1-hour intravenous infusion once every 21 days. Patients randomized to pemetrexed also received folic acid and vitamin B12. The study was designed to show that overall survival with pemetrexed was non-inferior to docetaxel, as the major efficacy outcome measure, and that overall survival was superior for patients randomized to pemetrexed compared to docetaxel, as a secondary outcome measure.

A total of 571 patients were enrolled with 283 patients randomized to pemetrexed and 288 patients randomized to docetaxel. The median age was 58 years (range 22 to 87 years); 72% were male; 71% were White, 24% were Asian, 2.8% were Black or African American, 1.8% were Hispanic or Latino, and <2% were other ethnicities; 88% had an ECOG PS of 0 or 1. With regard to tumor characteristics, 75% had Stage IV disease; 53% had adenocarcinoma, 30% had squamous histology; 8% large cell; and 9% had other histologic subtypes of NSCLC.

The efficacy results in the overall population and in subgroup analyses based on histologic subtype are provided in Tables 16 and 17, respectively. Study JMEI did not show an improvement in overall survival in the intent-to-treat population. In subgroup analyses, there was no evidence of a treatment effect on survival in patients with squamous NSCLC; the absence of a treatment effect in patients with NSCLC of squamous histology was also observed Studies JMDB and JMEN [see Clinical Studies (14.1)].

Table 16: Efficacy Results in Study JMEI
Efficacy Parameter | Pemetrexed; (N=283) | Docetaxel; (N=288)
Overall survival
Median (months) | 8.3 | 7.9
(95% CI) | (7.0 to 9.4) | (6.3 to 9.2)
Hazard ratioa | 0.99
(95% CI) | (0.82 to 1.20)
Progression-free survival
Median (months) | 2.9 | 2.9
(95% CI) | (2.4 to 3.1) | (2.7 to 3.4)
Hazard ratioa | 0.97
(95% CI) | (0.82 to 1.16)
Overall response rate | 8.5% | 8.3%
(95% CI) | (5.2 to 11.7) | (5.1 to 11.5)
a Hazard ratios are not adjusted for multiplicity or for stratification variables.

Table 17: Exploratory Efficacy Analyses by Histologic Subgroup in Study JMEI
Histologic Subgroups | Pemetrexed; (N=283) | Docetaxel; (N=288)
Non-squamous NSCLC (N=399)
Median (months) | 9.3 | 8.0
(95% CI) | (7.8 to 9.7) | (6.3 to 9.3)
HRa | 0.89
(95% CI) | (0.71 to 1.13)
Adenocarcinoma (N=301)
Median (months) | 9.0 | 9.2
(95% CI) | (7.6 to 9.6) | (7.5 to 11.3)
HRa | 1.09
(95% CI) | (0.83 to 1.44)
Large Cell (N=47)
Median (months) | 12.8 | 4.5
(95% CI) | (5.8 to 14.0) | (2.3 to 9.1)
HRa | 0.38
(95% CI) | (0.18 to 0.78)
Otherb (N=51)
Median (months) | 9.4 | 7.9
(95% CI) | (6.0 to 10.1) | (4.0 to 8.9)
HRa | 0.62
(95% CI) | (0.32 to 1.23)
Squamous NSCLC (N=172)
Median (months) | 6.2 | 7.4
(95% CI) | (4.9 to 8.0) | (5.6 to 9.5)
HRa | 1.32
(95% CI) | (0.93 to 1.86)
a Hazard ratio unadjusted for multiple comparisons.
b Primary diagnosis of NSCLC not specified as adenocarcinoma, large cell carcinoma, or squamous cell carcinoma.

14.2 Mesothelioma

The efficacy of pemetrexed was evaluated in Study JMCH (NCT00005636), a multicenter, randomized (1:1), single-blind study conducted in patients with MPM who had received no prior chemotherapy. Patients were randomized (n=456) to receive pemetrexed 500 mg/m^2 intravenously over 10 minutes followed 30 minutes later by cisplatin 75 mg/m^2 intravenously over two hours on Day 1 of each 21-day cycle or to receive cisplatin 75 mg/m^2 intravenously over 2 hours on Day 1 of each 21-day cycle; treatment continued until disease progression or intolerable toxicity. The study was modified after randomization and treatment of 117 patients to require that all patients receive folic acid 350 mcg to 1000 mcg daily beginning 1 to 3 weeks prior to the first dose of pemetrexed and continuing until 1 to 3 weeks after the last dose, vitamin B12 1000 mcg intramuscularly 1 to 3 weeks prior to first dose of pemetrexed and every 9 weeks thereafter, and dexamethasone 4 mg orally, twice daily, for 3 days starting the day prior to each pemetrexed dose. Randomization was stratified by multiple baseline variables including KPS, histologic subtype (epithelial, mixed, sarcomatoid, other), and gender. The major efficacy outcome measure was overall survival and additional efficacy outcome measures were time to disease progression, overall response rate, and response duration.

A total of 448 patients received at least one dose of protocol-specified therapy; 226 patients were randomized to and received at least one dose of pemetrexed plus cisplatin, and 222 patients were randomized to and received cisplatin. Among the 226 patients who received cisplatin with pemetrexed, 74% received full supplementation with folic acid and vitamin B12 during study therapy, 14% were never supplemented, and 12% were partially supplemented. Across the study population, the median age was 61 years (range: 20 to 86 years); 81% were male; 92% were White, 5% were Hispanic or Latino, 3.1% were Asian, and <1% were other ethnicities; and 54% had a baseline KPS score of 90-100% and 46% had a KPS score of 70-80%. With regard to tumor characteristics, 46% had Stage IV disease, 31% Stage III, 15% Stage II, and 7% Stage I disease at baseline; the histologic subtype of mesothelioma was epithelial in 68% of patients, mixed in 16%, sarcomatoid in 10% and other histologic subtypes in 6%. The baseline demographics and tumor characteristics of the subgroup of fully supplemented patients was similar to the overall study population.

The efficacy results from Study JMCH are summarized in Table 18 and Figure 9.

Table 18: Efficacy Results in Study JMCH
 | All Randomized and Treated |  | Fully Supplemented
 | Patients |  | Patients
Efficacy Parameter | (N=448) |  | (N=331)
 | Pemetrexed/Cisplatin | Cisplatin | Pemetrexed/Cisplatin | Cisplatin
 | (N=226) | (N=222) | (N=168) | (N=163)
Median overall survival (months) | 12.1 | 9.3 | 13.3 | 10.0
(95% CI) | (10.0 to 14.4) | (7.8 to 10.7) | (11.4 to 14.9) | (8.4 to 11.9)
Hazard ratioa | 0.77 |  | 0.75
Log rank p-value | 0.020 |  | NAb
a Hazard ratios are not adjusted for stratification variables.
b Not a pre-specified analysis.

Figure 9: Kaplan-Meier Curves for Overall Survival in Study JMCH

Based upon prospectively defined criteria (modified Southwest Oncology Group methodology) the objective tumor response rate for pemetrexed plus cisplatin was greater than the objective tumor response rate for cisplatin alone. There was also improvement in lung function (forced vital capacity) in the pemetrexed plus cisplatin arm compared to the control arm.

15 REFERENCES

1. “OSHA Hazardous Drugs.” OSHA. [https://www.osha.gov/hazardous-drugs]

16 HOW SUPPLIED/STORAGE AND HANDLING

How Supplied

Pemetrexed Injection is supplied as a clear, colorless to slightly yellowish or slightly yellow-greenish solution available in sterile single-dose vials at a 25 mg/mL concentration in the following package strengths.

Pemetrexed Injection 100 mg/4 mL (25 mg/mL) NDC 0480-4516-01

Pemetrexed Injection 500 mg/20 mL (25 mg/mL) NDC 0480-4514-01

Pemetrexed Injection 1 g/40 mL (25 mg/mL) NDC 0480-4515-01

Storage and Handling

Store under refrigeration between 2° to 8°C (36° to 46°F). Protect from light. Retain in carton until time of use.

Pemetrexed Injection is a hazardous drug. Follow applicable special handling and disposal procedures.^1

Do not Freeze.

Sterile, Nonpyrogenic, Preservative-free.

The vial stopper is not made with natural rubber latex.

17 PATIENT COUNSELING INFORMATION

Advise the patient to read the FDA-approved patient labeling (Patient Information).

Premedication and Concomitant Medication: Instruct patients to take folic acid as directed and to keep appointments for vitamin B12 injections to reduce the risk of treatment-related toxicity. Instruct patients of the requirement to take corticosteroids to reduce the risks of treatment-related toxicity [see Dosage and Administration (2.4) and Warnings and Precautions (5.1)].

Myelosuppression: Inform patients of the risk of low blood cell counts and instruct them to immediately contact their physician for signs of infection, fever, bleeding, or symptoms of anemia [see Warnings and Precautions (5.1)].

Renal Failure: Inform patients of the risks of renal failure, which may be exacerbated in patients with dehydration arising from severe vomiting or diarrhea. Instruct patients to immediately contact their healthcare provider for a decrease in urine output [see Warnings and Precautions (5.2)].

Bullous and Exfoliative Skin Disorders: Inform patients of the risks of severe and exfoliative skin disorders. Instruct patients to immediately contact their healthcare provider for development of bullous lesions or exfoliation in the skin or mucous membranes [see Warnings and Precautions (5.3)].

Interstitial Pneumonitis: Inform patients of the risks of pneumonitis. Instruct patients to immediately contact their healthcare provider for development of dyspnea or persistent cough [see Warnings and Precautions (5.4)].

Radiation Recall: Inform patients who have received prior radiation of the risks of radiation recall. Instruct patients to immediately contact their healthcare provider for development of inflammation or blisters in an area that was previously irradiated [see Warnings and Precautions (5.5)].

Increased Risk of Toxicity with Ibuprofen in Patients with Renal Impairment: Advise patients with mild to moderate renal impairment of the risks associated with concomitant ibuprofen use and instruct them to avoid use of all ibuprofen containing products for 2 days before, the day of, and 2 days following administration of Pemetrexed Injection [see Dosage and Administration (2.5), Warnings and Precautions (5.6), and Drug Interactions (7)].

Embryo-Fetal Toxicity: Advise females of reproductive potential and males with female partners of reproductive potential of the potential risk to a fetus [see Warnings and Precautions (5.7) and Use in Specific Populations (8.1)]. Advise females of reproductive potential to use effective contraception during treatment with Pemetrexed Injection and for 6 months after the last dose. Advise females to inform their prescriber of a known or suspected pregnancy. Advise males with female partners of reproductive potential to use effective contraception during treatment with Pemetrexed Injection and for 3 months after the last dose [see Warnings and Precautions (5.7) and Use in Specific Populations (8.3)].

Lactation: Advise women not to breastfeed during treatment with Pemetrexed Injection and for 1 week after the last dose [see Use in Specific Populations (8.2)].

Manufactured In Romania By:
Sindan Pharma SRL
Bucharest 1, Romania 011171

Manufactured For:
Teva Pharmaceuticals
Parsippany, NJ 07054

Rev. A 12/2022

PATIENT INFORMATION

Pemetrexed (pem" e trex' ed) Injection,
for intravenous use

What is Pemetrexed Injection?

Pemetrexed Injection is a prescription medicine used to treat:

- a kind of lung cancer called non-squamous non-small cell lung cancer (NSCLC). Pemetrexed Injection is used:
  - as the first treatment in combination with pembrolizumab and platinum chemotherapy when your lung cancer with no abnormal EGFR or ALK gene has spread (advanced NSCLC).
  - as the first treatment in combination with cisplatin when your lung cancer has spread (advanced NSCLC).
  - alone as maintenance treatment after you have received 4 cycles of chemotherapy that contains platinum for first treatment of your advanced NSCLC and your cancer has not progressed.
  - alone when your lung cancer has returned or spread after prior chemotherapy.

Pemetrexed Injection is not for use for the treatment of people with squamous cell, non-small cell lung cancer.

- a kind of cancer called malignant pleural mesothelioma. This cancer affects the lining of the lungs and chest wall. Pemetrexed Injection is used in combination with cisplatin as the first treatment for malignant pleural mesothelioma that cannot be removed by surgery or you are not able to have surgery.

Pemetrexed Injection has not been shown to be safe and effective in children.

Do not take Pemetrexed Injection: if you have had a severe allergic reaction to any medicine that contains pemetrexed.

Before taking Pemetrexed Injection, tell your healthcare provider about all of your medical conditions, including if you:

- have kidney problems.
- have had radiation therapy.
- are pregnant or plan to become pregnant. Pemetrexed Injection can harm your unborn baby.

Females who are able to become pregnant:

Your healthcare provider will check to see if you are pregnant before you start treatment with Pemetrexed Injection. You should use effective birth control (contraception) during treatment with Pemetrexed Injection and for 6 months after the last dose. Tell your healthcare provider right away if you become pregnant or think you are pregnant during treatment with Pemetrexed Injection.

Males with female partners who are able to become pregnant should use effective birth control (contraception) during treatment with Pemetrexed Injection and for 3 months after the last dose.

- are breastfeeding or plan to breastfeed. It is not known if pemetrexed passes into breast milk. Do not breastfeed during treatment with Pemetrexed Injection and for 1 week after the last dose.

Tell your healthcare provider about all the medicines you take, including prescription and over-the-counter medicines, vitamins, and herbal supplements.

Tell your healthcare provider if you have kidney problems and take a medicine that contains ibuprofen. You should avoid taking ibuprofen for 2 days before, the day of, and 2 days after receiving treatment with Pemetrexed Injection.

How is Pemetrexed Injection given?

- It is very important to take folic acid and vitamin B12 during your treatment with Pemetrexed Injection to lower your risk of harmful side effects.
  - Take folic acid exactly as prescribed by your healthcare provider 1 time a day, beginning 7 days (1 week) before your first dose of Pemetrexed Injection and continue taking folic acid until 21 days (3 weeks) after your last dose of Pemetrexed Injection.
  - Your healthcare provider will give you vitamin B12 injections during treatment with Pemetrexed Injection. You will get your first vitamin B12 injection 7 days (1 week) before your first dose of Pemetrexed Injection, and then every 3 cycles.
- Your healthcare provider will prescribe a medicine called corticosteroid for you to take 2 times a day for 3 days, beginning the day before each treatment with Pemetrexed Injection.
- Pemetrexed Injection is given to you by intravenous (IV) infusion into your vein. The infusion is given over 10 minutes.
- Pemetrexed Injection is usually given on Day 1 of each 21-day (3 weeks) cycle.

What are the possible side effects of Pemetrexed Injection?

Pemetrexed Injection can cause serious side effects, including:

- Low blood cell counts. Low blood cell counts can be severe, including low white blood cell counts (neutropenia), low platelet counts (thrombocytopenia), and low red blood cell counts (anemia). Your healthcare provider will do blood test to check your blood cell counts regularly during your treatment with Pemetrexed Injection. Tell your healthcare provider right away if you have any signs of infection, fever, bleeding, or severe tiredness during your treatment with Pemetrexed Injection.
- Kidney problems, including kidney failure. Pemetrexed Injection can cause severe kidney problems that can lead to death. Severe vomiting or diarrhea can lead to loss of fluids (dehydration) which may cause kidney problems to become worse. Tell your healthcare provider right away if you have a decrease in amount of urine.
- Severe skin reactions. Severe skin reactions that may lead to death can happen with Pemetrexed Injection. Tell your healthcare provider right away if you develop blisters, skin sores, skin peeling, or painful sores, or ulcers in your mouth, nose, throat or genital area.
- Lung problems (pneumonitis). Pemetrexed Injection can cause serious lung problems that can lead to death. Tell your healthcare provider right away if you get any new or worsening symptoms of shortness of breath, cough, or fever.
- Radiation recall. Radiation recall is a skin reaction that can happen in people who have received radiation treatment in the past and are treated with Pemetrexed Injection. Tell your healthcare provider if you get swelling, blistering, or a rash that looks like a sunburn in an area that was previously treated with radiation.

The most common side effects of Pemetrexed Injection when given alone are:

- tiredness ● nausea ● loss of appetite

The most common side effects of Pemetrexed Injection when given with cisplatin are:

● vomiting ● low white blood cell counts (neutropenia)

● swelling or sores in your mouth or sore throat ● low platelet counts (thrombocytopenia)

● constipation ● low red blood cell counts (anemia)

The most common side effects of Pemetrexed Injection when given with pembrolizumab and platinum chemotherapy are:

● tiredness/weakness ● nausea

● constipation ● diarrhea

● loss of appetite ● rash

● vomiting ● cough

● shortness of breath ● fever

Pemetrexed Injection may cause fertility problems in males. This may affect your ability to father a child. It is not known if these effects are reversible. Talk to your healthcare provider if this is a concern for you.

Your healthcare provider will do blood test to check for side effects during treatment with Pemetrexed Injection. Your healthcare provider may change your dose of Pemetrexed Injection, delay treatment, or stop treatment if you have certain side effects.

Tell your healthcare provider if you have any side effect that bothers you or that does not go away.

These are not all the side effects of Pemetrexed Injection. For more information, ask your healthcare provider or pharmacist. Call your doctor for medical advice about side effects. You may report side effects to FDA at 1-800-FDA-1088.

General information about the safe and effective use of Pemetrexed Injection.

Medicines are sometimes prescribed for purposes other than those listed in a Patient Information leaflet.

You can ask your pharmacist or healthcare provider for information about Pemetrexed Injection that is written for health professionals.

What are the ingredients in Pemetrexed Injection?
Active ingredient: pemetrexed
Inactive ingredients: tromethamine, citric acid anhydrous, methionine and water for injection.

Manufactured In Romania By: Sindan Pharma SRL, Bucharest 1, Romania 011171
Manufactured For: Teva Pharmaceuticals, Parsippany, NJ 07054
For more information, call Teva at 1-888-838-2872.

This Patient Information has been approved by the U.S. Food and Drug Administration. Rev. A 12/2022

PACKAGE LABEL.PRINCIPAL DISPLAY PANEL

NDC 0480-4516-01

Pemetrexed Injection
100 mg/4 mL
(25 mg/mL)

Must Dilute Before Intravenous Infusion

Do not mix with calcium-containing infusion solutions.

Store refrigerated

Discard unused portion.

CAUTION: Cytotoxic Agent

Rx Only

4 mL
Single-Dose Vial

PACKAGE LABEL.PRINCIPAL DISPLAY PANEL

NDC 0480-4514-01

Pemetrexed Injection
500 mg/20 mL
(25 mg/mL)

Must Dilute Before Intravenous Infusion

Do not mix with calcium-containing infusion solutions.

Store refrigerated

Discard unused portion.

CAUTION: Cytotoxic Agent

Rx Only

20 mL
Single-Dose Vial

PACKAGE LABEL.PRINCIPAL DISPLAY PANEL

NDC 0480-4515-01

Pemetrexed Injection
1 g/40 mL
(25 mg/mL)

Must Dilute Before Intravenous Infusion

Do not mix with calcium-containing infusion solutions.

Store refrigerated

Discard unused portion.

CAUTION: Cytotoxic Agent

Rx Only

40 mL
Single-Dose Vial